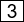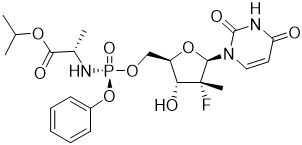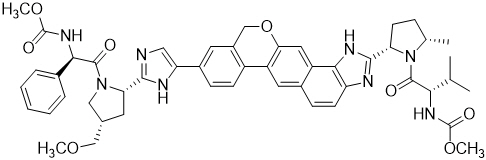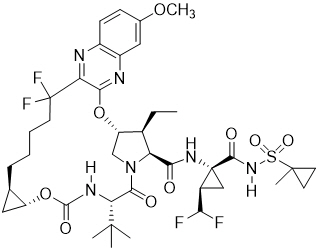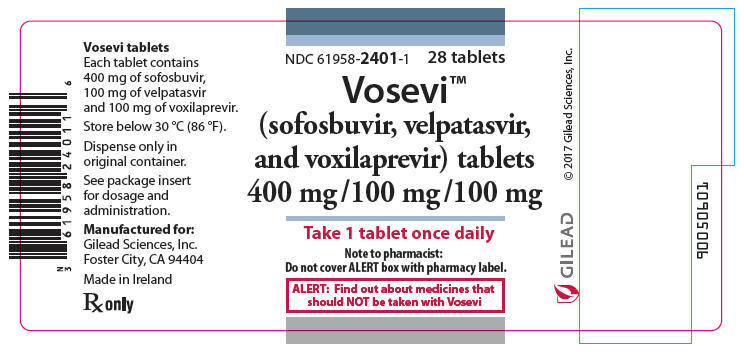 DRUG LABEL: Vosevi
NDC: 61958-2401 | Form: TABLET, FILM COATED
Manufacturer: Gilead Sciences, Inc.
Category: prescription | Type: HUMAN PRESCRIPTION DRUG LABEL
Date: 20250714

ACTIVE INGREDIENTS: SOFOSBUVIR 400 mg/1 1; VELPATASVIR 100 mg/1 1; VOXILAPREVIR 100 mg/1 1
INACTIVE INGREDIENTS: ALCOHOL; COPOVIDONE K25-31; MICROCRYSTALLINE CELLULOSE; CROSCARMELLOSE SODIUM; MAGNESIUM STEARATE; ACETONE; LACTOSE MONOHYDRATE; WATER; TITANIUM DIOXIDE; POLYETHYLENE GLYCOL 3350; TALC; FERRIC OXIDE RED; FERRIC OXIDE YELLOW; FERROSOFERRIC OXIDE; SILICON DIOXIDE; POLYVINYL ALCOHOL, UNSPECIFIED

HIGHLIGHTS OF PRESCRIBING INFORMATION

These highlights do not include all the information needed to use VOSEVI safely and effectively. See full prescribing information for VOSEVI.
VOSEVI® (sofosbuvir, velpatasvir, and voxilaprevir) tablets, for oral use
Initial U.S. Approval: 2017

WARNING: RISK OF HEPATITIS B VIRUS REACTIVATION IN PATIENTS COINFECTED WITH HCV AND HBV

See full prescribing information for complete boxed warning.

Hepatitis B virus (HBV) reactivation has been reported, in some cases resulting in fulminant hepatitis, hepatic failure, and death. (5.1)

RECENT MAJOR CHANGES

Dosage and Administration, Renal Impairment (2.3) | 11/2019
Warnings and Precautions, Risk of Hepatic Decompensation/Failure in Patients with Evidence of Advanced Liver Disease (5.2) | 09/2019

1 INDICATIONS AND USAGE

VOSEVI is a fixed-dose combination of sofosbuvir, a hepatitis C virus (HCV) nucleotide analog NS5B polymerase inhibitor, velpatasvir, an HCV NS5A inhibitor, and voxilaprevir, an HCV NS3/4A protease inhibitor, and is indicated for the treatment of adult patients with chronic HCV infection without cirrhosis or with compensated cirrhosis (Child-Pugh A) who have (1, 2.2, 14):

- genotype 1, 2, 3, 4, 5, or 6 infection and have previously been treated with an HCV regimen containing an NS5A inhibitor.
- genotype 1a or 3 infection and have previously been treated with an HCV regimen containing sofosbuvir without an NS5A inhibitor.
  - Additional benefit of VOSEVI over sofosbuvir/velpatasvir was not shown in adults with genotype 1b, 2, 4, 5, or 6 infection previously treated with sofosbuvir without an NS5A inhibitor.

2 DOSAGE AND ADMINISTRATION

- Testing: Prior to initiating VOSEVI, test all patients for HBV infection by measuring HBsAg and anti-HBc. (2.1)
- Recommended dosage: One tablet (400 mg of sofosbuvir, 100 mg of velpatasvir, and 100 mg of voxilaprevir) taken orally once daily with food. (2.2)
- See recommended treatment regimen and duration in table below (2.2):

Genotype | Patients Previously Treated with an HCV Regimen Containing: | VOSEVI Duration
1, 2, 3, 4, 5, or 6 | An NS5A inhibitor [In clinical trials, prior NS5A inhibitor experience included daclatasvir, elbasvir, ledipasvir, ombitasvir, or velpatasvir.] | 12 weeks
1a or 3 | Sofosbuvir without an NS5A inhibitor [In clinical trials, prior treatment experience included sofosbuvir with or without any of the following: peginterferon alfa/ribavirin, ribavirin, HCV NS3/4A protease inhibitor (boceprevir, simeprevir, or telaprevir).] | 12 weeks

- For patients with renal impairment including end stage renal disease on dialysis, follow the dosage recommendations in the table above. (2.3)
- VOSEVI is not recommended in patients with moderate or severe hepatic impairment (Child-Pugh B or C). (2.4, 5.2)

3 DOSAGE FORMS AND STRENGTHS

Tablets: 400 mg sofosbuvir, 100 mg velpatasvir, and 100 mg voxilaprevir (3)

4 CONTRAINDICATIONS

Coadministration with rifampin. (4)

5 WARNINGS AND PRECAUTIONS

- Risk of Hepatitis B Virus Reactivation: Test all patients for evidence of current or prior HBV infection before initiation of HCV treatment. Monitor HCV/HBV coinfected patients for HBV reactivation and hepatitis flare during HCV treatment and post-treatment follow-up. Initiate appropriate patient management for HBV infection as clinically indicated. (5.1)
- Risk of Hepatic Decompensation/Failure in Patients with Evidence of Advanced Liver Disease: Hepatic decompensation/failure, including fatal outcomes, have been reported mostly in patients with cirrhosis and baseline moderate or severe liver impairment (Child-Pugh B or C) treated with HCV NS3/4A protease inhibitor-containing regimens. Monitor for clinical and laboratory evidence of hepatic decompensation. Discontinue VOSEVI in patients who develop evidence of hepatic decompensation/failure. (5.2)
- Bradycardia with Amiodarone Coadministration: Serious symptomatic bradycardia may occur in patients taking amiodarone with VOSEVI, a sofosbuvir-containing regimen, particularly in patients also receiving beta blockers, or those with underlying cardiac comorbidities and/or advanced liver disease. Coadministration of amiodarone with VOSEVI is not recommended. In patients without alternative viable treatment options, cardiac monitoring is recommended. (5.3, 7.3)

6 ADVERSE REACTIONS

- The most common adverse reactions (incidence greater than or equal to 10%, all grades) observed with treatment with VOSEVI for 12 weeks were headache, fatigue, diarrhea, and nausea. (6.1)

To report SUSPECTED ADVERSE REACTIONS, contact Gilead Sciences, Inc. at 1-800-GILEAD-5 or FDA at 1-800-FDA-1088 or www.fda.gov/medwatch.

7 DRUG INTERACTIONS

- P-gp inducers and/or moderate to strong CYP inducers (e.g., St. John's wort, carbamazepine): May decrease concentrations of sofosbuvir, velpatasvir, and/or voxilaprevir. Use of VOSEVI with P-gp inducers and/or moderate to strong CYP inducers is not recommended. (5.4, 7)
- Consult the full prescribing information prior to use for potential drug interactions. (4, 5.3, 5.4, 7)
- Clearance of HCV infection with direct acting antivirals may lead to changes in hepatic function, which may impact safe and effective use of concomitant medications. Frequent monitoring of relevant laboratory parameters (INR or blood glucose) and dose adjustments of certain concomitant medications may be necessary. (7.3)

FULL PRESCRIBING INFORMATION

WARNING: RISK OF HEPATITIS B VIRUS REACTIVATION IN PATIENTS COINFECTED WITH HCV AND HBV

Test all patients for evidence of current or prior hepatitis B virus (HBV) infection before initiating treatment with VOSEVI. HBV reactivation has been reported in HCV/HBV coinfected patients who were undergoing or had completed treatment with HCV direct-acting antivirals (DAA) and were not receiving HBV antiviral therapy. Some cases have resulted in fulminant hepatitis, hepatic failure, and death. Monitor HCV/HBV coinfected patients for hepatitis flare or HBV reactivation during HCV treatment and post-treatment follow-up. Initiate appropriate patient management for HBV infection as clinically indicated [see Warnings and Precautions (5.1)].

1 INDICATIONS AND USAGE

VOSEVI is indicated for the treatment of adult patients with chronic hepatitis C virus (HCV) infection without cirrhosis or with compensated cirrhosis (Child-Pugh A) who have [see Dosage and Administration (2.2) and Clinical Studies (14)]:

- genotype 1, 2, 3, 4, 5, or 6 infection and have previously been treated with an HCV regimen containing an NS5A inhibitor.
- genotype 1a or 3 infection and have previously been treated with an HCV regimen containing sofosbuvir without an NS5A inhibitor.
  - Additional benefit of VOSEVI over sofosbuvir/velpatasvir was not shown in adults with genotype 1b, 2, 4, 5, or 6 infection previously treated with sofosbuvir without an NS5A inhibitor.

2 DOSAGE AND ADMINISTRATION

2.1 Testing Prior to the Initiation of Therapy

Test all patients for evidence of current or prior HBV infection by measuring hepatitis B surface antigen (HBsAg) and hepatitis B core antibody (anti-HBc) before initiating HCV treatment with VOSEVI [see Warnings and Precautions (5.1)].

2.2 Recommended Dosage

The recommended dosage of VOSEVI is one tablet, taken orally, once daily with food [see Clinical Pharmacology (12.3)]. One tablet of VOSEVI contains 400 mg of sofosbuvir, 100 mg of velpatasvir, and 100 mg of voxilaprevir. Table 1 shows the recommended treatment regimen and duration based on patient population.

Table 1 Recommended Treatment Regimen and Duration in Adults Without Cirrhosis or With Compensated Cirrhosis (Child-Pugh A)
Genotype | Patients Previously Treated with an HCV Regimen Containing: | VOSEVI Duration
1, 2, 3, 4, 5, or 6 | An NS5A inhibitor [In clinical trials, prior NS5A inhibitor experience included daclatasvir, elbasvir, ledipasvir, ombitasvir, or velpatasvir.] | 12 weeks
1a or 3 | Sofosbuvir without an NS5A inhibitor [In clinical trials, prior treatment experience included sofosbuvir with or without any of the following: peginterferon alfa/ribavirin, ribavirin, HCV NS3/4A protease inhibitor (boceprevir, simeprevir, or telaprevir).] | 12 weeks

2.3 Renal Impairment

No dosage adjustment of VOSEVI is recommended in patients with any degree of renal impairment including patients on dialysis [see Use in Specific Populations (8.6) and Clinical Pharmacology (12.3)].

2.4 Moderate or Severe Hepatic Impairment

VOSEVI is not recommended in patients with moderate or severe hepatic impairment (Child-Pugh B or C) due to higher exposures of voxilaprevir in these patients [see Warnings and Precautions (5.2), Use in Specific Populations (8.7), and Clinical Pharmacology (12.3)].

3 DOSAGE FORMS AND STRENGTHS

Each VOSEVI tablet contains 400 mg of sofosbuvir, 100 mg of velpatasvir, and 100 mg of voxilaprevir. The tablets are beige, capsule-shaped, film-coated, and debossed with "GSI" on one side and "" on the other side.

4 CONTRAINDICATIONS

VOSEVI is contraindicated with rifampin [see Drug Interactions (7.3), and Clinical Pharmacology (12.3)].

5 WARNINGS AND PRECAUTIONS

5.1 Risk of Hepatitis B Virus Reactivation in Patients Coinfected with HCV and HBV

Hepatitis B virus (HBV) reactivation has been reported in HCV/HBV coinfected patients who were undergoing or had completed treatment with HCV direct-acting antivirals, and who were not receiving HBV antiviral therapy. Some cases have resulted in fulminant hepatitis, hepatic failure, and death. Cases have been reported in patients who are HBsAg positive and also in patients with serologic evidence of resolved HBV infection (i.e., HBsAg negative and anti-HBc positive). HBV reactivation has also been reported in patients receiving certain immunosuppressant or chemotherapeutic agents; the risk of HBV reactivation associated with treatment with HCV direct-acting antivirals may be increased in these patients.

HBV reactivation is characterized as an abrupt increase in HBV replication manifesting as a rapid increase in serum HBV DNA level. In patients with resolved HBV infection reappearance of HBsAg can occur. Reactivation of HBV replication may be accompanied by hepatitis, i.e., increases in aminotransferase levels and, in severe cases, increases in bilirubin levels, liver failure, and death can occur.

Test all patients for evidence of current or prior HBV infection by measuring HBsAg and anti-HBc before initiating HCV treatment with VOSEVI. In patients with serologic evidence of HBV infection, monitor for clinical and laboratory signs of hepatitis flare or HBV reactivation during HCV treatment with VOSEVI and during post-treatment follow-up. Initiate appropriate patient management for HBV infection as clinically indicated.

5.2 Risk of Hepatic Decompensation/Failure in Patients with Evidence of Advanced Liver Disease

Postmarketing cases of hepatic decompensation/failure, including those with fatal outcomes, have been reported in patients treated with HCV NS3/4A protease inhibitor-containing regimens, including treatment with VOSEVI. Reported cases occurred in patients with baseline cirrhosis with and without moderate or severe liver impairment (Child-Pugh B or C). Because these events are reported voluntarily from a population of uncertain size, it is not always possible to reliably estimate their frequency or establish a causal relationship to drug exposure.

In patients with compensated cirrhosis (Child-Pugh A) or evidence of advanced liver disease such as portal hypertension, perform hepatic laboratory testing as clinically indicated; and monitor for signs and symptoms of hepatic decompensation such as the presence of jaundice, ascites, hepatic encephalopathy, and variceal hemorrhage. Discontinue VOSEVI in patients who develop evidence of hepatic decompensation/failure.

VOSEVI is not recommended in patients with moderate to severe hepatic impairment (Child-Pugh B or C) or those with any history of prior hepatic decompensation [see Dosage and Administration (2.4), Adverse Reactions (6.2), Use in Specific Populations (8.7), and Clinical Pharmacology (12.3)].

5.3 Serious Symptomatic Bradycardia When Coadministered with Amiodarone

Postmarketing cases of symptomatic bradycardia and cases requiring pacemaker intervention have been reported when amiodarone is coadministered with a sofosbuvir-containing regimen. A fatal cardiac arrest was reported in a patient taking amiodarone who was coadministered a sofosbuvir-containing regimen (HARVONI® (ledipasvir/sofosbuvir)). Bradycardia has generally occurred within hours to days, but cases have been observed up to 2 weeks after initiating HCV treatment. Patients also taking beta blockers, or those with underlying cardiac comorbidities and/or advanced liver disease may be at increased risk for symptomatic bradycardia with coadministration of amiodarone. Bradycardia generally resolved after discontinuation of HCV treatment. The mechanism for this effect is unknown.

Coadministration of amiodarone with VOSEVI is not recommended. For patients taking amiodarone who have no other alternative viable treatment options and who will be coadministered VOSEVI:

- Counsel patients about the risk of symptomatic bradycardia.
- Cardiac monitoring in an in-patient setting for the first 48 hours of coadministration is recommended, after which outpatient or self-monitoring of the heart rate should occur on a daily basis through at least the first 2 weeks of treatment.

Patients who are taking VOSEVI who need to start amiodarone therapy due to no other alternative viable treatment options should undergo similar cardiac monitoring as outlined above.

Due to amiodarone's long half-life, patients discontinuing amiodarone just prior to starting VOSEVI should also undergo similar cardiac monitoring as outlined above.

Patients who develop signs or symptoms of bradycardia should seek medical evaluation immediately. Symptoms may include near-fainting or fainting, dizziness or lightheadedness, malaise, weakness, excessive tiredness, shortness of breath, chest pains, confusion, or memory problems [see Adverse Reactions (6.2) and Drug Interactions (7.3)].

5.4 Risk of Reduced Therapeutic Effect Due to Concomitant Use of VOSEVI with Inducers of P-gp and/or Moderate to Strong Inducers of CYP

Drugs that are inducers of P-gp and/or moderate to strong inducers of CYP2B6, CYP2C8, or CYP3A4 (e.g., St. John's wort, carbamazepine) may significantly decrease plasma concentrations of sofosbuvir, velpatasvir, and/or voxilaprevir, leading to potentially reduced therapeutic effect of VOSEVI. The use of these agents with VOSEVI is not recommended [see Drug Interactions (7.3)].

6 ADVERSE REACTIONS

The following serious adverse reactions are described below and elsewhere in labeling:

- Serious Symptomatic Bradycardia When Coadministered with Amiodarone [see Warnings and Precautions (5.3)].

6.1 Clinical Trials Experience

Because clinical trials are conducted under widely varying conditions, adverse reaction rates observed in the clinical trials of a drug cannot be directly compared to rates in the clinical trials of another drug and may not reflect the rates observed in practice.

Adverse Reactions in HCV-Infected Subjects without Cirrhosis or with Compensated Cirrhosis

The adverse reactions data for VOSEVI were derived from two Phase 3 clinical trials (POLARIS-1 and POLARIS-4) that evaluated a total of 445 subjects infected with genotype 1, 2, 3, 4, 5, or 6 HCV, without cirrhosis or with compensated cirrhosis (Child-Pugh A), who received VOSEVI for 12 weeks. VOSEVI was studied in placebo- and active-controlled (sofosbuvir/velpatasvir) trials [see Clinical Studies (14.1 and 14.2)].

The proportion of subjects who permanently discontinued treatment due to adverse events was 0.2% for subjects who received VOSEVI for 12 weeks.

The most common adverse reactions (adverse events assessed as causally related by the investigator and at least 10%) were headache, fatigue, diarrhea, and nausea in subjects treated with VOSEVI for 12 weeks.

Table 2 lists adverse reactions (adverse events assessed as causally related by the investigator, all grades) observed in at least 5% of subjects receiving 12 weeks of treatment with VOSEVI in the Phase 3 clinical trials. The side-by-side tabulation is to simplify presentation; direct comparison across trials should not be made due to differing trial designs.

Table 2 Adverse Reactions (All Grades) Reported in ≥5% of Subjects With HCV Without Cirrhosis or With Compensated Cirrhosis Receiving VOSEVI in POLARIS-1 and POLARIS-4
 | POLARIS-1 |  | POLARIS-4
 | VOSEVI 12 weeks (N=263) | Placebo 12 weeks (N=152) | VOSEVI 12 weeks (N=182) | SOF/VEL 12 weeks (N=151)
Headache | 21% | 14% | 23% | 23%
Fatigue | 17% | 15% | 19% | 23%
Diarrhea | 13% | 9% | 14% | 3%
Nausea | 13% | 7% | 10% | 3%
Asthenia | 6% | 4% | 4% | 6%
Insomnia | 6% | 3% | 3% | 1%

In POLARIS-1, of the subjects receiving VOSEVI who experienced adverse reactions, 99% were mild or moderate (Grade 1 or 2) in severity. In POLARIS-4, of the subjects receiving VOSEVI who experienced adverse reactions, all the reported adverse reactions were mild or moderate (Grade 1 or 2) in severity.

Less Common Adverse Reactions Reported in Clinical Trials

The following adverse reactions occurred in less than 5% of subjects without cirrhosis or with compensated cirrhosis treated with VOSEVI for 12 weeks and are included because of a potential causal relationship.

Rash: In the POLARIS-1 and POLARIS-4 trials, rash occurred in less than 1% and 2% of subjects treated with VOSEVI, respectively. Rash was reported in 1% of subjects treated with placebo in POLARIS-1 and was not reported by any subject taking sofosbuvir/velpatasvir in POLARIS-4. No serious adverse reactions of rash occurred, and all rashes were mild or moderate in severity.

Depression: In the POLARIS-1 and POLARIS-4 trials, depressed mood occurred in less than 1% and 1% of subjects treated with VOSEVI, respectively. Depressed mood was not reported by any subject taking placebo in POLARIS-1 and was reported in 1% of subjects treated with sofosbuvir/velpatasvir in POLARIS-4. No serious adverse reactions of depressed mood occurred and all events were mild or moderate in severity.

Laboratory Abnormalities

Lipase Elevations: Isolated, asymptomatic lipase elevations of greater than 3×ULN were observed in POLARIS-1 in 2% of subjects treated with VOSEVI and 3% of subjects treated with placebo, and in POLARIS-4 in 2% of subjects treated with VOSEVI and less than 1% of subjects treated with sofosbuvir/velpatasvir.

Creatine Kinase: Isolated, asymptomatic creatine kinase elevations greater than or equal to 10×ULN were reported in POLARIS-1 in 1% of subjects treated with VOSEVI and 1% of subjects treated with placebo, and in POLARIS-4 in less than 1% of subjects treated with VOSEVI and no subjects treated with sofosbuvir/velpatasvir.

Total bilirubin: Increases in total bilirubin less than or equal to 1.5×ULN were observed in subjects treated with VOSEVI due to inhibition of OATP1B1 and OATP1B3 by voxilaprevir: 4% and 6% of subjects without cirrhosis in POLARIS-1 and POLARIS-4, respectively; and 7% and 13% of subjects with compensated cirrhosis in POLARIS-1 and POLARIS-4, respectively. No subjects experienced jaundice and total bilirubin levels decreased after completing VOSEVI treatment.

6.2 Postmarketing Experience

The following adverse reactions have been identified during post approval use of sofosbuvir-containing regimens. Because postmarketing reactions are reported voluntarily from a population of uncertain size, it is not always possible to reliably estimate their frequency or establish a causal relationship to drug exposure.

Hepatobiliary Disorders

Hepatic decompensation, hepatic failure with NS3/4A protease inhibitor-containing regimens [see Warnings and Precautions (5.2)].

Cardiac Disorders

Serious symptomatic bradycardia has been reported in patients taking amiodarone who initiated treatment with a sofosbuvir-containing regimen [see Warnings and Precautions (5.3) and Drug Interactions (7.3)].

Skin and Subcutaneous Tissue Disorders

Skin rashes, sometimes with blisters or angioedema-like swelling

Angioedema

7 DRUG INTERACTIONS

7.1 Potential for Other Drugs to Affect VOSEVI

Sofosbuvir, velpatasvir, and voxilaprevir are substrates of drug transporters P-gp and BCRP while GS-331007 (predominant circulating metabolite of sofosbuvir) is not. Voxilaprevir is also a substrate of OATP1B1 and OATP1B3. In vitro, slow metabolic turnover of velpatasvir by CYP2B6, CYP2C8, and CYP3A4 and of voxilaprevir by CYP1A2, CYP2C8, and primarily CYP3A4 was observed.

Drugs that are inducers of P-gp and/or moderate to strong inducers of CYP2B6, CYP2C8, or CYP3A4 (e.g., St. John's wort, carbamazepine) may significantly decrease plasma concentrations of sofosbuvir, velpatasvir, and/or voxilaprevir leading to reduced therapeutic effect of VOSEVI. The use of these agents with VOSEVI is not recommended [see Warnings and Precautions (5.4) and Clinical Pharmacology (12.3)]. VOSEVI may be coadministered with P-gp, BCRP, and CYP inhibitors. The use of OATP inhibitors which may substantially increase exposure of voxilaprevir (e.g., cyclosporine) with VOSEVI is not recommended [see Clinical Pharmacology (12.3)].

7.2 Potential for VOSEVI to Affect Other Drugs

Velpatasvir and voxilaprevir are inhibitors of drug transporters P-gp, BCRP, OATP1B1, and OATP1B3. Velpatasvir is also an inhibitor of OATP2B1. Coadministration of VOSEVI with drugs that are substrates of these transporters may alter the exposure of such drugs. Coadministration of VOSEVI with BCRP substrates (e.g., methotrexate, mitoxantrone, imatinib, irinotecan, lapatinib, rosuvastatin, sulfasalazine, topotecan) is not recommended [see Clinical Pharmacology (12.3)].

7.3 Established and Potentially Significant Drug Interactions

Clearance of HCV infection with direct acting antivirals may lead to changes in hepatic function, which may impact the safe and effective use of concomitant medications. For example, altered blood glucose control resulting in serious symptomatic hypoglycemia has been reported in diabetic patients in postmarketing case reports and published epidemiological studies. Management of hypoglycemia in these cases required either discontinuation or dose modification of concomitant medications used for diabetes treatment.

Frequent monitoring of relevant laboratory parameters (e.g., International Normalized Ratio [INR] in patients taking warfarin, blood glucose levels in diabetic patients) or drug concentrations of concomitant medications such as cytochrome P450 substrates with a narrow therapeutic index (e.g., certain immunosuppressants) is recommended to ensure safe and effective use. Dose adjustments of concomitant medications may be necessary.

Table 3 provides a listing of established or potentially clinically significant drug interactions. The drug interactions described are based on studies conducted with either VOSEVI, the components of VOSEVI (sofosbuvir, velpatasvir, and/or voxilaprevir), or are predicted drug interactions that may occur with VOSEVI [see Contraindications (4), Warnings and Precautions (5.3, 5.4), and Clinical Pharmacology (12.3)].

Table 3 Potentially Significant Drug Interactions: Alteration in Dose or Regimen May Be Recommended Based on Drug Interaction Studies or Predicted Interaction [This table is not all inclusive.]
Concomitant Drug Class: Drug Name | Effect on Concentration [↓ = decrease, ↑ = increase.] | Clinical Effect/Recommendation
Acid Reducing Agents: | ↓ velpatasvir | Velpatasvir solubility decreases as pH increases. Drugs that increase gastric pH are expected to decrease concentration of velpatasvir.
Antacids (e.g., aluminum and magnesium hydroxide) | ↓ velpatasvir | Separate antacid and VOSEVI administration by 4 hours.
H2-receptor antagonists (e.g., famotidine) [These interactions have been studied in healthy adults.] | ↓ velpatasvir | H2-receptor antagonists may be administered simultaneously with or staggered from VOSEVI at a dose that does not exceed doses comparable with famotidine 40 mg twice daily.
Proton-pump inhibitors (e.g., omeprazole) | ↓ velpatasvir | Omeprazole 20 mg can be administered with VOSEVI. Use with other proton pump-inhibitors has not been studied.
Antiarrhythmics:
amiodarone | Effect on amiodarone, sofosbuvir, velpatasvir, and voxilaprevir concentrations unknown | Coadministration of amiodarone with VOSEVI may result in serious symptomatic bradycardia. The mechanism of this effect is unknown. Coadministration of amiodarone with VOSEVI is not recommended; if coadministration is required, cardiac monitoring is recommended [see Warnings and Precautions (5.3)].
digoxin | ↑ digoxin | Therapeutic concentration monitoring of digoxin is recommended when coadministered with VOSEVI. Refer to digoxin prescribing information for monitoring and dose modification recommendations for concentration increases with unclear magnitude.
Anticoagulants:
dabigatran etexilate | ↑ dabigatran | Clinical monitoring of dabigatran is recommended when coadministered with VOSEVI. Refer to dabigatran etexilate prescribing information for dose modification recommendations in the setting of moderate renal impairment.
Anticonvulsants:
carbamazepine phenytoin phenobarbital | ↓ sofosbuvir ↓ velpatasvir ↓ voxilaprevir | Coadministration is not recommended.
Antimycobacterials:
rifampin | ↓ sofosbuvir ↓ velpatasvir ↑ voxilaprevir (single dose) ↓ voxilaprevir (multiple dose) | Coadministration with rifampin is contraindicated [see Contraindications (4)].
rifabutin rifapentine | ↓ sofosbuvir ↓ velpatasvir ↓ voxilaprevir | Coadministration is not recommended.
Antiretrovirals:
atazanavir lopinavir | ↑ voxilaprevir | Coadministration of VOSEVI with atazanavir- or lopinavir-containing regimens is not recommended.
tipranavir/ritonavir | ↓ sofosbuvir ↓ velpatasvir | Coadministration is not recommended. The effect on voxilaprevir is unknown.
efavirenz | ↓ velpatasvir ↓ voxilaprevir | Coadministration of VOSEVI with efavirenz-containing regimens is not recommended.
tenofovir disoproxil fumarate (tenofovir DF) | ↑ tenofovir | Monitor for tenofovir-associated adverse reactions in patients receiving VOSEVI concomitantly with a regimen containing tenofovir DF. Refer to the prescribing information of the tenofovir DF-containing product for recommendations on renal monitoring.
Herbal Supplements:
St. John's wort | ↓ sofosbuvir ↓ velpatasvir ↓ voxilaprevir | Coadministration is not recommended.
HMG-CoA Reductase Inhibitors:
pravastatin | ↑ pravastatin | Coadministration of VOSEVI with pravastatin has been shown to increase the concentration of pravastatin, which is associated with increased risk of myopathy, including rhabdomyolysis. Pravastatin may be administered with VOSEVI at a dose that does not exceed pravastatin 40 mg.
rosuvastatin | ↑ rosuvastatin | Coadministration of VOSEVI with rosuvastatin may significantly increase the concentration of rosuvastatin which is associated with increased risk of myopathy, including rhabdomyolysis. Coadministration of VOSEVI with rosuvastatin is not recommended.
pitavastatin | ↑ pitavastatin | Coadministration with VOSEVI may increase the concentration of pitavastatin and is not recommended, due to an increased risk of myopathy, including rhabdomyolysis.
atorvastatin fluvastatin lovastatin simvastatin | ↑ atorvastatin ↑ fluvastatin ↑ lovastatin ↑ simvastatin | Coadministration with VOSEVI may increase the concentrations of atorvastatin, fluvastatin, lovastatin, and simvastatin. Increased statin concentrations may increase the risk of myopathy, including rhabdomyolysis. Use the lowest approved statin dose. If higher doses are needed, use the lowest necessary statin dose based on a risk/benefit assessment.
Immunosuppressants:
cyclosporine | ↑ voxilaprevir | Coadministration of voxilaprevir with cyclosporine has been shown to substantially increase the plasma concentration of voxilaprevir, the safety of which has not been established. Coadministration of VOSEVI with cyclosporine is not recommended.

7.4 Drugs without Clinically Significant Interactions with VOSEVI

Based on drug interaction studies conducted with the components of VOSEVI (sofosbuvir, velpatasvir, and/or voxilaprevir) or VOSEVI, no clinically significant drug interactions have been observed with the following drugs [see Clinical Pharmacology (12.3)]:

- VOSEVI: cobicistat, darunavir, elvitegravir, emtricitabine, ethinyl estradiol/norgestimate, gemfibrozil, rilpivirine, ritonavir, tenofovir alafenamide, voriconazole
- Sofosbuvir/velpatasvir: dolutegravir, ketoconazole, raltegravir
- Sofosbuvir: methadone, tacrolimus

8 USE IN SPECIFIC POPULATIONS

8.1 Pregnancy

Risk Summary

No adequate human data are available to establish whether or not VOSEVI poses a risk to pregnancy outcomes. In animal reproduction studies, no evidence of adverse developmental outcomes was observed with the components of VOSEVI (sofosbuvir, velpatasvir, or voxilaprevir) at exposures greater than those in humans at the recommended human dose (RHD) [see Data]. During organogenesis in the mouse, rat, and rabbit, systemic exposures (AUC) of velpatasvir were approximately 23 (mice), 4 (rats), and 0.5 (rabbits) times the exposure in humans at the RHD, while exposures of voxilaprevir were approximately 141 (rats) and 4 (rabbits) times the exposure in humans at the RHD. Exposures of the predominant circulating metabolite of sofosbuvir (GS-331007) were approximately 6 (rats) and 16 (rabbits) times the exposure in humans at the RHD. In rat pre/postnatal development studies, maternal systemic exposures (AUC) for each component of VOSEVI were approximately 7 (sofosbuvir metabolite GS-331007), 3 (velpatasvir), and 238 (voxilaprevir) times the exposure in humans at the RHD.

The background risk of major birth defects and miscarriage for the indicated population is unknown. In the U.S. general population, the estimated background risk of major birth defects and miscarriage in clinically recognized pregnancies is 2–4% and 15–20%, respectively.

Data

Sofosbuvir: Sofosbuvir was administered orally to pregnant rats (up to 500 mg/kg/day) and rabbits (up to 300 mg/kg/day) on gestation days 6 to 18 and 6 to 19, respectively, and also to rats (oral doses up to 500 mg/kg/day) from gestation day 6 to lactation/post-partum day 20. No significant effects on embryo-fetal (rats and rabbits) or pre/postnatal (rats) development were observed at the highest doses tested. The systemic exposures (AUC) of the predominant circulating metabolite of sofosbuvir (GS-331007) during gestation were approximately 6 (rats) and 16 (rabbits) times the exposure in humans at the RHD.

Velpatasvir: Velpatasvir was administered orally to pregnant mice (up to 1000 mg/kg/day), rats (up to 200 mg/kg/day) and rabbits (up to 300 mg/kg/day) from gestation days 6 to 15, 6 to 17, and 7 to 20, respectively, and also to rats (oral doses up to 200 mg/kg) on gestation day 6 to lactation/post-partum day 20. No significant effects on embryo-fetal (mice, rats, and rabbits) or pre/postnatal (rats) development were observed at the highest doses tested. The systemic exposures (AUC) of velpatasvir during gestation were approximately 23 (mice), 4 (rats), and 0.5 (rabbits) times the exposure in humans at the RHD.

Voxilaprevir: Voxilaprevir was administered orally to pregnant rats (up to 100 mg/kg/day) and rabbits (up to 600 mg/kg/day) from gestation days 6 to 17, and 7 to 19, respectively, and also to rats (oral doses up to 100 mg/kg) on gestation day 6 to lactation/post-partum day 20. No significant effects on embryo-fetal (rats and rabbits) or pre/postnatal (rats) development were observed at the highest doses tested. The systemic exposures (AUC) of voxilaprevir during gestation were approximately 141 (rats) and 4 (rabbits) times the exposure in humans at the RHD.

8.2 Lactation

Risk Summary

It is not known whether the components of VOSEVI and its metabolites are present in human breast milk, affect human milk production, or have effects on the breastfed infant. When the components of VOSEVI were administered to lactating rats, GS-331007 (the predominant circulating metabolite of sofosbuvir) and velpatasvir were detected in milk, while voxilaprevir was detected in the plasma of nursing pups likely due to the presence of voxilaprevir in milk. No significant effects of any of the drugs were observed in nursing rat pups [see Data].

The developmental and health benefits of breastfeeding should be considered along with the mother's clinical need for VOSEVI and any potential adverse effects on the breastfed child from VOSEVI or from the underlying maternal condition.

Data

Sofosbuvir: No significant effects of sofosbuvir on growth or postnatal development were observed in nursing pups at the highest dose tested in rats. Maternal systemic exposure (AUC) of the predominant circulating metabolite of sofosbuvir (GS-331007) was approximately 7 times the exposure in humans at the RHD, with exposure of approximately 2% that of maternal exposure observed in nursing pups on lactation day 10. In a lactation study, sofosbuvir metabolites (primarily GS-331007) were excreted into the milk of lactating rats following administration of a single oral dose of sofosbuvir (20 mg/kg) on lactation day 2, with milk concentrations of approximately 10% that of maternal plasma concentrations observed 1 hour post-dose.

Velpatasvir: No significant effects of velpatasvir on growth or postnatal development were observed in nursing pups at the highest dose tested in rats. Maternal systemic exposure (AUC) of velpatasvir was approximately 3 times the exposure in humans at the RHD. Velpatasvir was present in the milk (approximately 173% that of maternal plasma concentrations) of lactating rats following a single oral dose of velpatasvir (30 mg/kg), and systemic exposure (AUC) in nursing pups was approximately 4% that of maternal exposure on lactation day 10.

Voxilaprevir: No significant effects of voxilaprevir on growth or postnatal development were observed in nursing pups at the highest dose tested in rats. Maternal systemic exposure (AUC) of voxilaprevir was approximately 238 times the exposure in humans at the RHD, with exposure of approximately 58% that of maternal exposure observed in nursing pups on lactation day 10.

8.4 Pediatric Use

Safety and effectiveness of VOSEVI have not been established in pediatric patients.

8.5 Geriatric Use

Clinical trials of VOSEVI included 74 subjects aged 65 and over (17% of total number of subjects in the POLARIS-1 and POLARIS-4 Phase 3 clinical trials). No overall differences in safety or effectiveness were observed between these subjects and younger subjects, and other reported clinical experience has not identified differences in responses between the elderly and younger patients, but greater sensitivity of some older individuals cannot be ruled out. No dosage adjustment of VOSEVI is warranted in geriatric patients [see Clinical Pharmacology (12.3)].

8.6 Renal Impairment

No dosage adjustment of VOSEVI is recommended for patients with mild, moderate, or severe renal impairment, including ESRD requiring dialysis [see Dosage and Administration (2.3) and Clinical Pharmacology (12.3)].

8.7 Hepatic Impairment

No dosage adjustment of VOSEVI is recommended for patients with mild hepatic impairment (Child-Pugh A). VOSEVI is not recommended in patients with moderate or severe hepatic impairment (Child-Pugh B or C) due to the higher exposures of voxilaprevir (up to 6-fold in non-HCV infected subjects); the safety and efficacy have not been established in HCV-infected patients with moderate or severe hepatic impairment [see Dosage and Administration (2.4) and Clinical Pharmacology (12.3)]. Postmarketing cases of hepatic decompensation/failure have been reported in these patients [see Warnings and Precautions (5.2)].

10 OVERDOSAGE

No specific antidote is available for overdose with VOSEVI. If overdose occurs the patient must be monitored for evidence of toxicity. Treatment of overdose with VOSEVI consists of general supportive measures including monitoring of vital signs as well as observation of the clinical status of the patient. Hemodialysis can efficiently remove the predominant circulating metabolite of sofosbuvir, GS-331007, with an extraction ratio of 53%. Hemodialysis is unlikely to result in significant removal of velpatasvir or voxilaprevir since velpatasvir and voxilaprevir are highly bound to plasma protein.

11 DESCRIPTION

VOSEVI is a fixed-dose combination tablet containing sofosbuvir, velpatasvir, and voxilaprevir for oral administration. Sofosbuvir is a nucleotide analog HCV NS5B polymerase inhibitor, velpatasvir is an NS5A inhibitor, and voxilaprevir is an NS3/4A protease inhibitor.

Each tablet contains 400 mg sofosbuvir, 100 mg velpatasvir, and 100 mg of voxilaprevir. The tablets include the following inactive ingredients: colloidal silicon dioxide, copovidone, croscarmellose sodium, lactose monohydrate, magnesium stearate, and microcrystalline cellulose. The tablets are film-coated with a coating material containing the following inactive ingredients: ferrosoferric oxide, iron oxide red, iron oxide yellow, polyethylene glycol, polyvinyl alcohol, talc, and titanium dioxide.

Sofosbuvir: The IUPAC name for sofosbuvir is (S)-Isopropyl 2-((S)-(((2R,3R,4R,5R)-5-(2,4-dioxo-3,4-dihydropyrimidin-1(2H)-yl)-4-fluoro-3-hydroxy-4-methyltetrahydrofuran-2-yl)methoxy)-(phenoxy)phosphorylamino)propanoate. It has a molecular formula of C22H29FN3O9P and a molecular weight of 529.45. It has the following structural formula:

Sofosbuvir is a white to off-white crystalline solid with a solubility of at least 2 mg/mL across the pH range of 2–7.7 at 37 °C and is slightly soluble in water.

Velpatasvir: The IUPAC name for velpatasvir is Methyl {(1R)-2-[(2S,4S)-2-(5-{2-[(2S,5S)-1-{(2S)-2-[(methoxycarbonyl)amino]-3-methylbutanoyl}-5-methylpyrrolidin-2-yl]-1,11-dihydro[2]benzopyrano[4',3':6,7]naphtho[1,2-d]imidazol-9-yl}-1H-imidazol-2-yl)-4-(methoxymethyl)pyrrolidin-1-yl]-2-oxo-1-phenylethyl}carbamate. It has a molecular formula of C49H54N8O8 and a molecular weight of 883.0. It has the following structural formula:

Velpatasvir is practically insoluble (less than 0.1 mg/mL) above pH 5, slightly soluble (3.6 mg/mL) at pH 2, and soluble (greater than 36 mg/mL) at pH 1.2.

Voxilaprevir: The IUPAC name for voxilaprevir is (1aR,5S,8S,9S,10R,22aR)-5-tert-butyl-N-{(1R,2R)-2-(difluoromethyl)-1-[(1-methylcyclopropanesulfonyl) carbamoyl]cyclopropyl}-9-ethyl-18,18-difluoro-14-methoxy-3,6-dioxo-1,1a,3,4,5,6,9,10,18,19,20,21,22,22a-tetradecahydro-8H-7,10-methanocyclopropa[18,19][1,10,3,6]dioxadiazacyclononadecino[11,12-b]quinoxaline-8-carboxamide. It has a molecular formula of C40H52F4N6O9S and a molecular weight of 868.9. It has the following structural formula:

Voxilaprevir is a white to light brown solid. It is slightly hygroscopic to hygroscopic. Voxilaprevir is practically insoluble (less than 0.1 mg/mL) below pH 6.8.

12 CLINICAL PHARMACOLOGY

12.1 Mechanism of Action

VOSEVI is a fixed-dose combination of sofosbuvir, velpatasvir, and voxilaprevir which are DAA agents against the hepatitis C virus [see Microbiology (12.4)].

12.2 Pharmacodynamics

Cardiac Electrophysiology

The effect of sofosbuvir 400 mg (recommended dosage) and 1200 mg (3 times the recommended dosage) on QTc interval was evaluated in an active-controlled (moxifloxacin 400 mg) thorough QT trial. At a dose 3 times the recommended dose, sofosbuvir does not prolong QTc to any clinically relevant extent.

The effect of velpatasvir 500 mg (5 times the recommended dosage) was evaluated in an active-controlled (moxifloxacin 400 mg) thorough QT trial. At a dose 5 times the recommended dose, velpatasvir does not prolong QTc interval to any clinically relevant extent.

The effect of voxilaprevir 900 mg (9 times the recommended dosage) was evaluated in an active-controlled (moxifloxacin 400 mg) thorough QT trial. At a dose 9 times the recommended dose, voxilaprevir does not prolong QTc interval to any clinically relevant extent.

12.3 Pharmacokinetics

The pharmacokinetic properties of the components of VOSEVI are provided in Table 4. The multiple dose pharmacokinetic parameters of sofosbuvir and its metabolite GS-331007, velpatasvir, and voxilaprevir are provided in Table 5.

Table 4 Pharmacokinetic Properties of the Components of VOSEVI
 | Sofosbuvir | Velpatasvir | Voxilaprevir
Absorption
Tmax (h) | 2 | 4 | 4
Effect of food (relative to fasting) [Values refer to geometric mean systemic exposure. VOSEVI should be taken with food.] | ↑ 64% to 144% | ↑ 40% to 166% | ↑ 112% to 435%
Distribution
% Bound to human plasma proteins | 61–65 | >99 | >99
Blood-to-plasma ratio | 0.7 | 0.5–0.7 | 0.5–0.8
Metabolism
Metabolism | Cathepsin A CES1 HINT1 | CYP2B6 CYP2C8 CYP3A4 | CYP3A4
Elimination
Major route of elimination | SOF: metabolism GS-331007 [GS-331007 is the primary circulating nucleotide metabolite of SOF.] : glomerular filtration and active tubular secretion | Biliary excretion | Biliary excretion
t1/2 (h) [t1/2 values refer to median terminal plasma half-life.] | SOF: 0.5 GS-331007: 29 | 17 | 33
% Of dose excreted in urine [Single dose administration of [^14C] SOF, [^14C] VEL, [^14C] VOX in mass balance studies.] | 80 [Predominantly as GS-331007.] | 0.4 | 0
% Of dose excreted in feces | 14 | 94 (77% [Percent of dose.] as parent) | 94 (40% as parent)
CES1 = carboxylesterase 1; HINT1 = histidine triad nucleotide-binding protein 1.

Table 5 Multiple Dose Pharmacokinetic Parameters of Sofosbuvir and its Metabolite, GS-331007, Velpatasvir, and Voxilaprevir Following Oral Administration in HCV-Infected Adults
Parameter Mean (%CV) | Sofosbuvir [From Population PK analysis, N = 1038] | GS-331007 [From Population PK analysis, N = 1593] | Velpatasvir [From Population PK analysis, N = 1595] | Voxilaprevir [From Population PK analysis, N = 1591]
Cmax (nanogram per mL) | 678 (35.4) | 744 (28.3) | 311 (56.1) | 192 (85.8)
AUCtau (nanogram∙hr per mL) | 1665 (30.1) | 12834 (29.0) | 4041 (48.6) | 2577 (73.7)
Ctrough (nanogram per mL) | NA | NA | 51 (64.7) | 47 (82.0)
CV = coefficient of variation; NA = not applicable.

Sofosbuvir and GS-331007 AUC0–24 and Cmax were similar in healthy adult subjects and subjects with HCV infection. Relative to healthy subjects (N=137), velpatasvir AUC0–24 and Cmax were 41% lower and 39% lower, respectively, in HCV-infected subjects. Relative to healthy subjects (N=63), voxilaprevir AUC0–24 and Cmax were both 260% higher in HCV-infected subjects.

Sofosbuvir and GS-331007 AUCs are near dose-proportional over the dose range of 200 mg to 1200 mg. Velpatasvir AUC increases in a greater than proportional manner from 5 to 50 mg and in a less than proportional manner from 50 to 450 mg in healthy volunteers. However, velpatasvir exhibited near dose-proportional increase in exposures 25 mg to 150 mg in HCV-infected patients. Voxilaprevir AUC increases in a greater than proportional manner over the dose range of 100 to 900 mg when administered with food.

Specific Populations

Pediatric Patients: The pharmacokinetics of VOSEVI in pediatric patients has not been established [see Use in Specific Populations (8.4)].

Geriatric Patients: Population pharmacokinetic analysis in HCV-infected subjects showed that within the age range (18 to 85 years) analyzed, age did not have a clinically relevant effect on the exposure to sofosbuvir, GS-331007, velpatasvir, or voxilaprevir [see Use in Specific Populations (8.5)].

Patients with Renal Impairment:

The pharmacokinetics of sofosbuvir were studied in HCV-negative subjects with mild (eGFR between 50 to less than 80 mL/min/1.73 m^2), moderate (eGFR between 30 to less than 50 mL/min/1.73 m^2), severe renal impairment (eGFR less than 30 mL/min/1.73 m^2), and subjects with ESRD requiring hemodialysis following a single 400 mg dose of sofosbuvir. Relative to subjects with normal renal function (eGFR greater than 80 mL/min/1.73 m^2), the sofosbuvir AUC0–inf was 61%, 107%, and 171% higher in subjects with mild, moderate, and severe renal impairment, while the GS-331007 AUC0–inf was 55%, 88%, and 451% higher, respectively. In subjects with ESRD, relative to subjects with normal renal function, sofosbuvir and GS-331007 AUC0–inf was 28% and 1280% higher when sofosbuvir was dosed 1 hour before hemodialysis compared with 60% and 2070% higher when sofosbuvir was dosed 1 hour after hemodialysis, respectively. A 4-hour hemodialysis session removed approximately 18% of administered dose of sofosbuvir [see Dosage and Administration (2.3) and Use in Specific Populations (8.6)].

The pharmacokinetics of velpatasvir were studied with a single dose of 100 mg velpatasvir in HCV-negative subjects with severe renal impairment (eGFR less than 30 mL/min by Cockcroft-Gault). No clinically relevant differences in velpatasvir pharmacokinetics were observed between healthy subjects and subjects with severe renal impairment.

The pharmacokinetics of voxilaprevir were studied with a single dose of 100 mg voxilaprevir in HCV-negative subjects with severe renal impairment (eGFR < 30 mL/min by Cockcroft-Gault). No clinically relevant differences in voxilaprevir pharmacokinetics were observed between healthy subjects and subjects with severe renal impairment.

The pharmacokinetics of sofosbuvir, GS-331007, and velpatasvir were studied in HCV-infected subjects with ESRD requiring dialysis treated with once daily sofosbuvir/velpatasvir 400/100 mg for 12 weeks. The results were consistent with those observed in HCV negative subjects with ESRD requiring dialysis. The pharmacokinetics of voxilaprevir have not been studied in subjects with ESRD. However, voxilaprevir exposure following administration of VOSEVI is not expected to be meaningfully altered in HCV-infected subjects with ESRD requiring dialysis compared to subjects with normal renal function.

Patients with Hepatic Impairment:

The pharmacokinetics of sofosbuvir were studied following 7-day dosing of 400 mg sofosbuvir in HCV-infected subjects with moderate and severe hepatic impairment (Child-Pugh B and C). Relative to subjects with normal hepatic function, the sofosbuvir AUC0–24 was 126% and 143% higher in subjects with moderate and severe hepatic impairment, respectively, while the GS-331007 AUC0–24 was 18% and 9% higher, respectively. Population pharmacokinetic analysis in HCV-infected subjects indicated that compensated cirrhosis (Child-Pugh A) had no clinically relevant effect on the exposure of sofosbuvir and GS-331007.

The pharmacokinetics of velpatasvir were studied with a single dose of 100 mg velpatasvir in HCV-negative subjects with moderate and severe hepatic impairment (Child-Pugh B and C). Velpatasvir plasma exposure (AUCinf) was similar in subjects with moderate hepatic impairment, severe hepatic impairment, and control subjects with normal hepatic function. Population pharmacokinetic analysis in HCV-infected subjects indicated that compensated cirrhosis (Child-Pugh A) had no clinically relevant effect on the exposure of velpatasvir.

The pharmacokinetics of voxilaprevir were studied with a single dose of 100 mg voxilaprevir in HCV-negative subjects with moderate and severe hepatic impairment (Child-Pugh B and C). Relative to subjects with normal hepatic function, the voxilaprevir AUCinf was 299% and 500% higher in subjects with moderate and severe hepatic impairment, respectively. Population pharmacokinetic analysis in HCV-infected subjects indicated that subjects with compensated cirrhosis (Child-Pugh A) had 73% higher exposure of voxilaprevir than those without cirrhosis [see Dosage and Administration (2.4) and Use in Specific Populations (8.7)].

Race and Gender: Population pharmacokinetics analysis in HCV-infected subjects indicated that race and gender had no clinically relevant effect on the exposure of sofosbuvir, GS-331007, velpatasvir, or voxilaprevir.

Drug Interaction Studies

After oral administration of VOSEVI, sofosbuvir is rapidly absorbed and subject to extensive first-pass hepatic extraction (hydrolysis followed by sequential phosphorylation) to form the pharmacologically active triphosphate. In clinical pharmacology studies, both sofosbuvir and the primary circulating metabolite GS-331007 (dephosphorylated nucleotide metabolite) were monitored for purposes of pharmacokinetic analyses.

Sofosbuvir, velpatasvir, and voxilaprevir are substrates of drug transporters P-gp and BCRP while GS-331007 is not. Voxilaprevir, and to a lesser extent velpatasvir, are also substrates of OATP1B1 and OATP1B3. In vitro, slow metabolic turnover of velpatasvir by CYP2B6, CYP2C8, and CYP3A4 and of voxilaprevir by CYP1A2, CYP2C8, and primarily CYP3A4 was observed. Inducers of P-gp and/or moderate to strong inducers of CYP2B6, CYP2C8, or CYP3A4 (e.g., St. John's wort, carbamazepine) may significantly decrease plasma concentrations of sofosbuvir, velpatasvir, and/or voxilaprevir leading to reduced therapeutic effect of VOSEVI [see Contraindications (4), Warnings and Precautions (5.4), and Drug Interactions (7.3)]. Coadministration with drugs that inhibit P-gp and/or BCRP may increase sofosbuvir, velpatasvir, and/or voxilaprevir plasma concentrations without increasing GS-331007 plasma concentration. Coadministration with drugs that inhibit OATP may increase voxilaprevir plasma concentrations. Drugs that inhibit CYP2B6, CYP2C8, or CYP3A4 may increase plasma concentration of velpatasvir and/or voxilaprevir.

Sofosbuvir and GS-331007 are not inhibitors of drug transporters P-gp, BCRP, OATP1B1, OATP1B3, or OCT1 and GS-331007 is not an inhibitor of OAT1, OAT3, OCT2, or MATE1. Sofosbuvir and GS-331007 are not inhibitors or inducers of CYP or UGT1A1 enzymes.

Velpatasvir is an inhibitor of drug transporters P-gp, BCRP, OATP1B1, OATP1B3, and OATP2B1, and its involvement in drug interactions with these transporters is primarily limited to the process of absorption. At clinically relevant concentrations, velpatasvir is not an inhibitor of hepatic transporters OATP1A2 or OCT1, renal transporters OCT2, OAT1, OAT3 or MATE1, or CYP or UGT1A1 enzymes.

Voxilaprevir is an inhibitor of drug transporters P-gp, BCRP, OATP1B1, and OATP1B3, and its involvement in drug interactions with these transporters is primarily limited to the process of absorption. At clinically relevant concentrations, voxilaprevir is not an inhibitor of hepatic transporters OCT1, renal transporters OCT2, OAT1, OAT3, or MATE1, or CYP or UGT1A1 enzymes.

The effects of coadministered drugs on the exposure of sofosbuvir, GS-331007, velpatasvir, and voxilaprevir are shown in Table 6. The effects of sofosbuvir, velpatasvir, voxilaprevir, sofosbuvir/velpatasvir, or VOSEVI on the exposure of coadministered drugs are shown in Table 7 [see Drug Interactions (7)].

Table 6 Drug Interactions: Changes in Pharmacokinetic Parameters for Sofosbuvir, GS-331007, Velpatasvir, and Voxilaprevir in the Presence of the Coadministered Drug [All interaction studies conducted in healthy volunteers.]
Coadministered Drug |  | Sofosbuvir (SOF)/ Velpatasvir (VEL)/Voxilaprevir (VOX) |  | N | Geometric Mean Ratio (90% CI) of Sofosbuvir, GS-331007, Velpatasvir, and Voxilaprevir PK With/Without Coadministered Drug No Effect=1.00
Drug | Dosage (mg) | Active Component | Dosage (mg) | N | Geometric Mean Ratio (90% CI) of Sofosbuvir, GS-331007, Velpatasvir, and Voxilaprevir PK With/Without Coadministered Drug No Effect=1.00
Drug | Dosage (mg) | Active Component | Dosage (mg) | N | Component | Cmax | AUC | Cmin
Atazanavir + ritonavir | 300 + 100 single dose | SOF/VEL/VOX | 400/100/100 single dose | 15 | sofosbuvir | 1.29 (1.09, 1.52) | 1.40 (1.25, 1.57) | NA
Atazanavir + ritonavir | 300 + 100 single dose | SOF/VEL/VOX | 400/100/100 single dose | 15 | GS-331007 | 1.05 (0.99, 1.12) | 1.25 (1.16, 1.36) | NA
Atazanavir + ritonavir | 300 + 100 single dose | SOF/VEL/VOX | 400/100/100 single dose | 15 | velpatasvir | 1.29 (1.07, 1.56) | 1.93 (1.58, 2.36) | NA
Atazanavir + ritonavir | 300 + 100 single dose | SOF/VEL/VOX | 400/100/100 single dose | 15 | voxilaprevir | 4.42 (3.65, 5.35) | 4.31 (3.76, 4.93) | NA
Carbamazepine | 300 twice daily | SOF | 400 single dose | 24 | sofosbuvir | 0.52 (0.43, 0.62) | 0.52 (0.46, 0.59) | NA
Carbamazepine | 300 twice daily | SOF | 400 single dose | 24 | GS-331007 | 1.04 (0.97, 1.11) | 0.99 (0.94, 1.04) | NA
Cyclosporine | 600 single dose | SOF | 400 single dose | 19 | sofosbuvir | 2.54 (1.87, 3.45) | 4.53 (3.26, 6.30) | NA
Cyclosporine | 600 single dose | SOF | 400 single dose | 19 | GS-331007 | 0.60 (0.53, 0.69) | 1.04 (0.90, 1.20) | NA
Cyclosporine | 600 single dose | VEL | 100 single dose | 12 | velpatasvir | 1.56 (1.22, 2.01) | 2.03 (1.51, 2.71) | NA
Cyclosporine | 600 single dose | VOX | 100 single dose | 25 | voxilaprevir | 19.02 (14.12, 25.62) | 9.39 (7.37, 11.96) | NA
Darunavir + ritonavir + emtricitabine/ tenofovir DF | 800 + 100 + 200/300 once daily | SOF/VEL/VOX + VOX | 400/100/100 + 100 once daily | 29 | sofosbuvir | 0.70 (0.62, 0.78) | 0.78 (0.73, 0.83) | NA
Darunavir + ritonavir + emtricitabine/ tenofovir DF | 800 + 100 + 200/300 once daily | SOF/VEL/VOX + VOX | 400/100/100 + 100 once daily | 29 | GS-331007 | 1.06 (1.01, 1.10) | 1.15 (1.12, 1.19) | NA
Darunavir + ritonavir + emtricitabine/ tenofovir DF | 800 + 100 + 200/300 once daily | SOF/VEL/VOX + VOX | 400/100/100 + 100 once daily | 29 | velpatasvir | 0.78 (0.73, 0.84) | 0.95 (0.88, 1.02) | 1.16 (1.07, 1.26)
Darunavir + ritonavir + emtricitabine/ tenofovir DF | 800 + 100 + 200/300 once daily | SOF/VEL/VOX + VOX | 400/100/100 + 100 once daily | 29 | voxilaprevir | 1.72 (1.51, 1.97) | 2.43 (2.15, 2.75) | 4.00 (3.44, 4.65)
Dolutegravir | 50 once daily | SOF/VEL | 400/100 once daily | 24 | sofosbuvir | 0.88 (0.80, 0.98) | 0.92 (0.85, 0.99) | NA
Dolutegravir | 50 once daily | SOF/VEL | 400/100 once daily | 24 | GS-331007 | 1.01 (0.93, 1.10) | 0.99 (0.97, 1.01) | 0.99 (0.97, 1.01)
Dolutegravir | 50 once daily | SOF/VEL | 400/100 once daily | 24 | velpatasvir | 0.94 (0.86, 1.02) | 0.91 (0.84, 0.98) | 0.88 (0.82, 0.94)
Efavirenz/emtricitabine/tenofovir DF [Administered as ATRIPLA® (efavirenz, emtricitabine, and tenofovir DF fixed-dose combination).] | 600/200/300 once daily | SOF/VEL | 400/100 once daily | 14 | sofosbuvir | 1.38 (1.14, 1.67) | 0.97 (0.83, 1.14) | NA
Efavirenz/emtricitabine/tenofovir DF [Administered as ATRIPLA® (efavirenz, emtricitabine, and tenofovir DF fixed-dose combination).] | 600/200/300 once daily | SOF/VEL | 400/100 once daily | 14 | GS-331007 | 0.86 (0.80, 0.93) | 0.90 (0.85, 0.96) | 1.01 (0.95, 1.07)
Efavirenz/emtricitabine/tenofovir DF [Administered as ATRIPLA® (efavirenz, emtricitabine, and tenofovir DF fixed-dose combination).] | 600/200/300 once daily | SOF/VEL | 400/100 once daily | 14 | velpatasvir | 0.53 (0.43, 0.64) | 0.47 (0.39, 0.57) | 0.43 (0.36, 0.52)
Elvitegravir/cobicistat/ emtricitabine/tenofovir alafenamide [Administered as GENVOYA® (elvitegravir, cobicistat, emtricitabine, and tenofovir alafenamide fixed-dose combination).] | 150/150/200/ 10 once daily | SOF/VEL/VOX + VOX | 400/100/100 + 100 once daily | 29 | sofosbuvir | 1.27 (1.09, 1.48) | 1.22 (1.12, 1.32) | NA
Elvitegravir/cobicistat/ emtricitabine/tenofovir alafenamide [Administered as GENVOYA® (elvitegravir, cobicistat, emtricitabine, and tenofovir alafenamide fixed-dose combination).] | 150/150/200/ 10 once daily | SOF/VEL/VOX + VOX | 400/100/100 + 100 once daily | 29 | GS-331007 | 1.28 (1.25, 1.32) | 1.43 (1.39, 1.47) | NA
Elvitegravir/cobicistat/ emtricitabine/tenofovir alafenamide [Administered as GENVOYA® (elvitegravir, cobicistat, emtricitabine, and tenofovir alafenamide fixed-dose combination).] | 150/150/200/ 10 once daily | SOF/VEL/VOX + VOX | 400/100/100 + 100 once daily | 29 | velpatasvir | 0.96 (0.89, 1.04) | 1.16 (1.06, 1.27) | 1.46 (1.30, 1.64)
Elvitegravir/cobicistat/ emtricitabine/tenofovir alafenamide [Administered as GENVOYA® (elvitegravir, cobicistat, emtricitabine, and tenofovir alafenamide fixed-dose combination).] | 150/150/200/ 10 once daily | SOF/VEL/VOX + VOX | 400/100/100 + 100 once daily | 29 | voxilaprevir | 1.92 (1.63, 2.26) | 2.71 (2.30, 3.19) | 4.50 (3.68, 5.50)
Ketoconazole | 200 twice daily | VEL | 100 single dose | 12 | velpatasvir | 1.29 (1.02, 1.64) | 1.71 (1.35, 2.18) | NA
Methadone | 30 to 130 daily | SOF | 400 once daily | 14 | sofosbuvir | 0.95 (0.68, 1.33) | 1.30 (1.00, 1.69) | NA
Methadone | 30 to 130 daily | SOF | 400 once daily | 14 | GS-331007 | 0.73 (0.65, 0.83) | 1.04 (0.89, 1.22) | NA
Omeprazole | 20 once daily 2 hours prior to VOSEVI | SOF/VEL/VOX | 400/100/100 single dose | 34 | sofosbuvir | 0.77 (0.65, 0.91) | 0.73 (0.67, 0.79) | NA
Omeprazole | 20 once daily 2 hours prior to VOSEVI | SOF/VEL/VOX | 400/100/100 single dose | 34 | GS-331007 | 1.27 (1.20, 1.34) | 0.97 (0.94, 1.01) | NA
Omeprazole | 20 once daily 2 hours prior to VOSEVI | SOF/VEL/VOX | 400/100/100 single dose | 34 | velpatasvir | 0.43 (0.38, 0.49) | 0.46 (0.41, 0.52) | NA
Omeprazole | 20 once daily 2 hours prior to VOSEVI | SOF/VEL/VOX | 400/100/100 single dose | 34 | voxilaprevir | 0.76 (0.69, 0.85) | 0.80 (0.74, 0.87) | NA
Omeprazole | 20 once daily 4 hours after VOSEVI | SOF/VEL/ VOX | 400/100/100 single dose | 34 | sofosbuvir | 0.94 (0.83, 1.06) | 0.82 (0.77, 0.87) | NA
Omeprazole | 20 once daily 4 hours after VOSEVI | SOF/VEL/ VOX | 400/100/100 single dose | 34 | GS-331007 | 1.19 (1.13, 1.26) | 0.99 (0.97, 1.01) | NA
Omeprazole | 20 once daily 4 hours after VOSEVI | SOF/VEL/ VOX | 400/100/100 single dose | 34 | velpatasvir | 0.49 (0.43, 0.55) | 0.49 (0.43, 0.55) | NA
Omeprazole | 20 once daily 4 hours after VOSEVI | SOF/VEL/ VOX | 400/100/100 single dose | 34 | voxilaprevir | 1.08 (0.96, 1.22) | 0.95 (0.88, 1.03) | NA
Rifabutin | 300 once daily | SOF | 400 single dose | 20 | Sofosbuvir | 0.64 (0.53, 0.77) | 0.76 (0.63, 0.91) | NA
Rifabutin | 300 once daily | SOF | 400 single dose | 20 | GS-331007 | 1.15 (1.03, 1.27) | 1.03 (0.95, 1.12) | NA
Rifampin | 600 once daily | SOF | 400 single dose | 17 | sofosbuvir | 0.23 (0.19, 0.29) | 0.28 (0.24, 0.32) | NA
Rifampin | 600 once daily | SOF | 400 single dose | 17 | GS-331007 | 1.23 (1.14, 1.34) | 0.95 (0.88, 1.03) | NA
Rifampin | 600 once daily | VEL | 100 single dose | 12 | velpatasvir | 0.29 (0.23, 0.37) | 0.18 (0.15, 0.22) | NA
Rifampin | 600 once daily | VOX | 100 single dose | 24 | voxilaprevir | 0.91 (0.76, 1.10) | 0.27 (0.23, 0.31) | NA
Rifampin | 600 single dose | VEL | 100 single dose | 12 | velpatasvir | 1.28 (1.05, 1.56) | 1.46 (1.17, 1.83) | NA
Rifampin | 600 single dose | VOX | 100 single dose | 24 | voxilaprevir | 11.10 (8.23, 14.98) | 7.91 (6.20, 10.09) | NA
Tacrolimus | 5 single dose | SOF | 400 single dose | 16 | sofosbuvir | 0.97 (0.65, 1.43) | 1.13 (0.81, 1.57) | NA
Tacrolimus | 5 single dose | SOF | 400 single dose | 16 | GS-331007 | 0.97 (0.83, 1.14) | 1.00 (0.87, 1.13) | NA
Voriconazole | 200 twice daily | VOX | 100 single dose | 24 | voxilaprevir | 1.13 (0.98, 1.31) | 1.84 (1.66, 2.03) | NA
NA = not available/not applicable, ND = not dosed.

No effect on the pharmacokinetic parameters of sofosbuvir, GS-331007, velpatasvir, or voxilaprevir was observed with the combination of emtricitabine, rilpivirine, and tenofovir alafenamide; famotidine; gemfibrozil; or the combination of raltegravir, emtricitabine, and tenofovir DF.

Table 7 Changes in Pharmacokinetic Parameters for Coadministered Drug in the Presence of Sofosbuvir, Velpatasvir, Voxilaprevir, or VOSEVI [All interaction studies conducted in healthy volunteers.]
Coadministered Drug |  | Sofosbuvir (SOF)/ Velpatasvir (VEL)/Voxilaprevir (VOX) |  | N | Geometric Mean Ratio (90% CI) of Coadministered Drug PK With/Without Sofosbuvir, Velpatasvir, Voxilaprevir, or VOSEVI No Effect=1.00
Drug | Dosage (mg) | Active Component | Dosage (mg) | N | Geometric Mean Ratio (90% CI) of Coadministered Drug PK With/Without Sofosbuvir, Velpatasvir, Voxilaprevir, or VOSEVI No Effect=1.00
Drug | Dosage (mg) | Active Component | Dosage (mg) | N | Cmax | AUC | Cmin
Atorvastatin | 40 single dose | SOF/VEL | 400/100 once daily | 26 | 1.68 (1.49, 1.89) | 1.54 (1.45, 1.64) | NA
Cyclosporine | 600 single dose | SOF | 400 single dose | 19 | 1.06 (0.94, 1.18) | 0.98 (0.85, 1.14) | NA
Cyclosporine | 600 single dose | VEL | 100 single dose | 12 | 0.92 (0.82, 1.02) | 0.88 (0.78, 1.00) | NA
Cyclosporine | 600 single dose | VOX | 100 single dose | 24 | 0.95 (0.88, 1.03) | 0.94 (0.84, 1.06) | NA
Dabigatran etexilate | 75 single dose | SOF/VEL/VOX + VOX | 400/100/100 + 100 once daily | 36 | 2.87 (2.61, 3.15) | 2.61 (2.41, 2.82) | NA
Darunavir + ritonavir + emtricitabine/tenofovir DF [Comparison based on exposures when administered as darunavir + ritonavir + emtricitabine/tenofovir DF.] | darunavir 800 once daily | SOF/VEL/VOX + VOX | 400/100/100 + 100 once daily | 29 | 0.89 (0.85, 0.94) | 0.86 (0.81, 0.91) | 0.66 (0.58, 0.74)
Darunavir + ritonavir + emtricitabine/tenofovir DF [Comparison based on exposures when administered as darunavir + ritonavir + emtricitabine/tenofovir DF.] | ritonavir 100 once daily | SOF/VEL/VOX + VOX | 400/100/100 + 100 once daily | 29 | 1.60 (1.47, 1.75) | 1.45 (1.35, 1.57) | 0.80 (0.72, 0.89)
Darunavir + ritonavir + emtricitabine/tenofovir DF [Comparison based on exposures when administered as darunavir + ritonavir + emtricitabine/tenofovir DF.] | emtricitabine 200 once daily | SOF/VEL/VOX + VOX | 400/100/100 + 100 once daily | 29 | 0.88 (0.82, 0.94) | 0.99 (0.96, 1.03) | 1.20 (1.15, 1.26)
Darunavir + ritonavir + emtricitabine/tenofovir DF [Comparison based on exposures when administered as darunavir + ritonavir + emtricitabine/tenofovir DF.] | tenofovir DF 300 once daily | SOF/VEL/VOX + VOX | 400/100/100 + 100 once daily | 29 | 1.48 (1.36, 1.61) | 1.39 (1.32, 1.46) | 1.47 (1.38, 1.56)
Digoxin | 0.25 single dose | VEL | 100 once daily | 21 | 1.88 (1.71, 2.08) | 1.34 (1.13, 1.60) | NA
Efavirenz/emtricitabine/tenofovir DF [Administered as ATRIPLA (efavirenz, emtricitabine, and tenofovir DF fixed-dose combination).] | efavirenz 600 once daily | SOF/VEL | 400/100 once daily | 15 | 0.81 (0.74, 0.89) | 0.85 (0.80, 0.91) | 0.90 (0.85, 0.95)
Efavirenz/emtricitabine/tenofovir DF [Administered as ATRIPLA (efavirenz, emtricitabine, and tenofovir DF fixed-dose combination).] | emtricitabine 200 once daily | SOF/VEL | 400/100 once daily | 15 | 1.07 (0.98, 1.18) | 1.07 (1.00, 1.14) | 1.10 (0.97, 1.25)
Efavirenz/emtricitabine/tenofovir DF [Administered as ATRIPLA (efavirenz, emtricitabine, and tenofovir DF fixed-dose combination).] | tenofovir DF 300 once daily | SOF/VEL | 400/100 once daily | 15 | 1.77 (1.53, 2.04) | 1.81 (1.68, 1.94) | 2.21 (2.00, 2.43)
Elvitegravir/cobicistat/ emtricitabine/tenofovir alafenamide [Administered as GENVOYA (elvitegravir, cobicistat, emtricitabine, and tenofovir alafenamide fixed-dose combination).] | elvitegravir 150 once daily | SOF/VEL/VOX + VOX | 400/100/100 + 100 once daily | 29 | 0.79 (0.75, 0.85) | 0.94 (0.88, 1.00) | 1.32 (1.17, 1.49)
Elvitegravir/cobicistat/ emtricitabine/tenofovir alafenamide [Administered as GENVOYA (elvitegravir, cobicistat, emtricitabine, and tenofovir alafenamide fixed-dose combination).] | cobicistat 150 once daily | SOF/VEL/VOX + VOX | 400/100/100 + 100 once daily | 29 | 1.23 (1.18, 1.28) | 1.50 (1.44, 1.58) | 3.50 (3.01, 4.07)
Elvitegravir/cobicistat/ emtricitabine/tenofovir alafenamide [Administered as GENVOYA (elvitegravir, cobicistat, emtricitabine, and tenofovir alafenamide fixed-dose combination).] | emtricitabine 200 once daily | SOF/VEL/VOX + VOX | 400/100/100 + 100 once daily | 29 | 0.87 (0.84, 0.91) | 0.96 (0.94, 0.99) | 1.14 (1.09, 1.20)
Elvitegravir/cobicistat/ emtricitabine/tenofovir alafenamide [Administered as GENVOYA (elvitegravir, cobicistat, emtricitabine, and tenofovir alafenamide fixed-dose combination).] | tenofovir alafenamide 10 once daily | SOF/VEL/VOX + VOX | 400/100/100 + 100 once daily | 29 | 0.79 (0.68, 0.92) | 0.93 (0.85, 1.01) | NA
Emtricitabine/rilpivirine/tenofovir alafenamide [Administered as ODEFSEY® (emtricitabine, rilpivirine, and tenofovir alafenamide fixed-dose combination).] | emtricitabine 200 once daily | SOF/VEL/VOX + VOX | 400/100/100 + 100 once daily | 30 | 0.88 (0.83, 0.93) | 0.93 (0.90, 0.96) | 1.07 (1.01, 1.14)
Emtricitabine/rilpivirine/tenofovir alafenamide [Administered as ODEFSEY® (emtricitabine, rilpivirine, and tenofovir alafenamide fixed-dose combination).] | rilpivirine 25 once daily | SOF/VEL/VOX + VOX | 400/100/100 + 100 once daily | 30 | 0.79 (0.74, 0.84) | 0.80 (0.76, 0.85) | 0.82 (0.77, 0.87)
Emtricitabine/rilpivirine/tenofovir alafenamide [Administered as ODEFSEY® (emtricitabine, rilpivirine, and tenofovir alafenamide fixed-dose combination).] | tenofovir alafenamide 25 once daily | SOF/VEL/VOX + VOX | 400/100/100 + 100 once daily | 30 | 1.32 (1.17, 1.48) | 1.52 (1.43, 1.61) | NA
Pravastatin | 40 single dose | SOF/VEL/VOX + VOX | 400/100/100 + 100 once daily | 19 | 1.89 (1.53, 2.34) | 2.16 (1.79, 2.60) | NA
Rosuvastatin | 10 single dose | SOF/VEL/VOX + VOX | 400/100/100 + 100 once daily | 19 | 18.88 (16.23, 21.96) | 7.39 (6.68, 8.18) | NA
Raltegravir + emtricitabine/tenofovir DF | emtricitabine 200 once daily | SOF/VEL | 400/100 once daily | 30 | 1.08 (1.04, 1.12) | 1.05 (1.03, 1.07) | 1.02 (0.97, 1.08)
Raltegravir + emtricitabine/tenofovir DF | tenofovir DF 300 once daily | SOF/VEL | 400/100 once daily | 30 | 1.46 (1.39, 1.54) | 1.40 (1.34, 1.45) | 1.70 (1.61, 1.79)
Raltegravir + emtricitabine/tenofovir DF | raltegravir 400 twice daily | SOF/VEL | 400/100 once daily | 30 | 1.03 (0.74, 1.43) | 0.97 (0.73, 1.28) | 0.79 (0.42, 1.48)
Tacrolimus | 5 single dose | SOF | 400 once daily | 16 | 0.73 (0.59, 0.90) | 1.09 (0.84, 1.40) | NA
NA = not available/not applicable.

No effect on the pharmacokinetic parameters of the following coadministered drugs was observed with VOSEVI (ethinyl estradiol/norgestimate) or its components sofosbuvir/velpatasvir (dolutegravir) or sofosbuvir (methadone).

12.4 Microbiology

Mechanism of Action

Sofosbuvir is an inhibitor of the HCV NS5B RNA-dependent RNA polymerase, which is required for viral replication. Sofosbuvir is a nucleotide prodrug that undergoes intracellular metabolism to form the pharmacologically active uridine analog triphosphate (GS-461203), which can be incorporated into HCV RNA by the NS5B polymerase and acts as a chain terminator. In a biochemical assay, GS-461203 inhibited the polymerase activity of the recombinant NS5B from HCV genotype 1b, 2a, 3a, and 4a with an IC50 value ranging from 0.36 to 3.3 µM. GS-461203 is neither an inhibitor of human DNA and RNA polymerases nor an inhibitor of mitochondrial RNA polymerase.

Velpatasvir is an inhibitor of the HCV NS5A protein, which is required for viral replication. Resistance selection in cell culture and cross-resistance studies indicate velpatasvir targets NS5A as its mode of action.

Voxilaprevir is a noncovalent, reversible inhibitor of the NS3/4A protease, which is necessary for the proteolytic cleavage of the HCV encoded polyprotein (into mature forms of the NS3, NS4A, NS4B, NS5A, and NS5B proteins) and is essential for viral replication. In a biochemical inhibition assay, voxilaprevir inhibited the proteolytic activity of recombinant NS3/4A enzymes from clinical isolates of HCV genotypes 1b and 3a with Ki values of 38 and 66 pM, respectively.

Antiviral Activity

In HCV replicon assays, sofosbuvir had median EC50 values of 15–110 nM against full-length or chimeric laboratory isolates and clinical isolates from subtypes 1a, 1b, 2a, 2b, 3a, 4a, 4d, 5a, and 6a. Velpatasvir had median EC50 values of 0.002–0.13 nM against full-length or chimeric laboratory isolates and clinical isolates from subtypes 1a, 1b, 2a, 2b, 3a, 4a, 4d, 4r, 5a, 6a, and 6e. Voxilaprevir had median EC50 values of 0.2–6.6 nM against full-length or chimeric laboratory isolates and clinical isolates from subtypes 1a, 1b, 2a, 2b, 3a, 4a, 4d, 4r, 5a, 6a, 6e, and 6n.

Evaluation of sofosbuvir in combination with velpatasvir or voxilaprevir, as well as the combination of velpatasvir and voxilaprevir, showed no antagonistic effect in reducing HCV RNA levels in replicon cells.

Resistance

In Cell Culture

HCV replicons with reduced susceptibility to sofosbuvir have been selected in cell culture for multiple genotypes including 1b, 2a, 2b, 3a, 4a, 5a, and 6a. Reduced susceptibility to sofosbuvir was associated with the nucleotide analog NS5B polymerase inhibitor resistance substitution, S282T, in all replicon genotypes examined. An M289L substitution emerged along with the S282T substitution in genotypes 2a, 5, and 6 replicons. Site-directed mutagenesis of the S282T substitution in replicons of genotype 1 to 6 conferred 2- to 18-fold reduced susceptibility to sofosbuvir.

HCV genotype 1a, 1b, 2a, 3a, 4a, 5a, and 6a replicon variants with reduced susceptibility to velpatasvir were selected in cell culture. The replicon variants developed amino acid substitutions at NS5A inhibitor resistance-associated positions 24, 28, 30, 31, 32, 58, 92, and 93. Phenotypic analysis of site-directed mutant replicons of the selected NS5A substitutions showed that single Y93H/N and the combination of L31V + Y93H/N in genotype 1a, the combination of L31V + Y93H in genotype 1b, the single substitution Y93H/S in genotype 3a, and single substitutions L31V and P32A/L/Q/R in genotype 6 conferred greater than 100-fold reduction in velpatasvir susceptibility. In the genotype 2a replicon, the single substitutions F28S and Y93H showed 91-fold and 46-fold reduced susceptibility to velpatasvir, respectively. The single substitution Y93H conferred 3-fold reduced susceptibility to velpatasvir in genotype 4a replicons. Combinations of these NS5A substitutions often showed greater reductions in susceptibility to velpatasvir than single substitutions alone.

HCV genotype 1a, 1b, 2a, 3a, 4a, 5a, and 6a replicon variants with reduced susceptibility to voxilaprevir were selected in cell culture. Amino acid substitutions were selected at NS3/4A protease inhibitor resistance-associated positions 41, 156, and 168. Site-directed mutagenesis of NS3 resistance-associated substitutions showed that substitutions conferring a greater than 100-fold reduction in voxilaprevir susceptibility were A156L/T in genotype 1a, A156T/V in genotype 1b, A156L/V in genotype 2a, A156T/V in genotype 3a, and A156L/T/V in genotype 4. Combinations of these NS3 substitutions often showed greater reductions in susceptibility to voxilaprevir than single substitutions alone.

In Clinical Trials

Of the 263 NS5A inhibitor-experienced subjects treated with VOSEVI for 12 weeks in POLARIS-1, 7 of 263 (3%) subjects (2 with genotype 1a, 4 with genotype 3a, and 1 with genotype 4d) did not achieve SVR12 and qualified for resistance analysis; 6 relapsed and 1 experienced virologic breakthrough. All the virologic failures had cirrhosis and all had a previous DAA regimen containing sofosbuvir; 3 were previously treated with ledipasvir/sofosbuvir, 2 were previously treated with sofosbuvir/velpatasvir, and 2 were previously treated with daclatasvir and sofosbuvir. Six of the 7 virologic failures had baseline NS5A inhibitor resistance-associated substitutions at position 30 or 93. All 7 virologic failures had NS5A resistance-associated substitutions at failure using a sensitivity threshold of 1% of the viral population.

Of the 2 genotype 1a virologic failure subjects, one subject with virologic breakthrough at Week 12 had virus with the NS5A resistance-associated substitution Q30T at baseline and failure and emergent NS5A resistance-associated substitutions L31M and Y93H at breakthrough; the other subject had virus with the NS5A resistance-associated substitution Y93N at baseline and relapse and emergence of low-level K24R (1.2%) in NS5A and V36A (2%) in NS3 at relapse.

Of the 4 genotype 3a virologic failure subjects, one subject had virus with emergent NS5A resistance-associated substitution E92K. Two subjects had virus with Y93H at relapse that was enriched from baseline. The remaining subject had virus with the NS5A resistance-associated substitution A30K at baseline and relapse and emergence of low-level Q41K (2%), V55A (3%), and R155M (1%) substitutions in NS3 at relapse.

The genotype 4d subject who relapsed had virus with emergent NS5A resistance-associated substitution Y93H.

No NS5B nucleotide analog inhibitor resistance-associated substitutions emerged among the virologic failure subjects from POLARIS-1.

In POLARIS-4, of the 182 DAA-experienced subjects who had not received an NS5A inhibitor treated with VOSEVI for 12 weeks, 1 subject (genotype 1a) of 182 (1%) subjects relapsed and qualified for resistance analysis. The NS5A resistance-associated substitution M28T (7.5%) emerged in this subject at relapse. No NS3/4A protease inhibitor or nucleotide analog NS5B inhibitor substitutions were observed in this subject at relapse.

Persistence of Resistance-Associated Substitutions

No data are available on the persistence of sofosbuvir, velpatasvir, or voxilaprevir resistance-associated substitutions. NS5A inhibitor resistance-associated substitutions observed with administration of other NS5A inhibitors have been found to persist for longer than 1 year in most patients. The long-term clinical impact of the emergence or persistence of virus containing sofosbuvir, velpatasvir, or voxilaprevir resistance-associated substitutions is unknown.

Effect of Baseline HCV Variants on Treatment Response

Analyses were conducted to explore the association between SVR12 rates and preexisting baseline NS3/4A protease inhibitor and NS5A inhibitor resistance-associated substitutions for subjects in POLARIS-1 and POLARIS-4. Amino acid positions considered in resistance analyses included NS3 positions 36, 41, 43, 54, 55, 56, 155, 156, and 168, and NS5A positions 24, 28, 30, 31, 58, 92, or 93. Baseline resistance-associated amino acid substitutions, which may include natural polymorphisms or prior treatment-emergent substitutions relative to subtype-specific references, were identified by next generation sequencing analysis using a sensitivity threshold of 15% of the viral population.

Overall, the presence of baseline NS3/4A protease inhibitor, NS5A inhibitor, and nucleotide analog NS5B polymerase inhibitor resistance-associated substitutions did not alter the SVR rates for DAA-experienced subjects in the POLARIS-1 and POLARIS-4 trials who received 12 weeks of VOSEVI. For subjects treated with VOSEVI for 12 weeks, SVR12 rates in subjects with or without baseline NS3 and NS5A resistance-associated substitutions in the POLARIS-1 and POLARIS-4 trials were all greater than or equal to 97%.

In POLARIS 1, which included NS5A inhibitor-experienced subjects, 79% (206/260) of subjects had baseline NS5A resistance-associated substitutions across all genotypes. The most prevalent NS5A resistance-associated substitutions were at primary resistance-associated amino acid positions 30 (97/206; 47%), 31 (58/206; 28%), and 93 (103/206; 50%). Fifty-five percent (n=113/206) of the subjects had a single NS5A resistance-associated substitution, while 2 resistance-associated substitutions were detected in 65/206 subjects (32%) and 3 or more were detected in 28/206 subjects (14%). Overall prevalence of NS3/4A protease inhibitor resistance-associated substitutions across all genotypes was 15% (37/248). The most prevalent NS3 resistance-associated substitutions were at positions 36 (5/17; 29%) and 168 (7/17; 41%) in genotype 1a and position 56 in genotype 1b (8/12; 67%). Substitutions at positions 36, 56, or 168 were detected in 1-2 subjects for each genotype 2, 3, or 4.

In POLARIS-4, which included DAA-experienced subjects who had not received an NS5A inhibitor, 32% (57/177) of subjects who received 12 weeks of VOSEVI had baseline NS5A inhibitor resistance-associated substitutions. Most of the subjects had a single NS5A resistance-associated substitution (n=40; 70%). The most prevalent NS5A resistance-associated substitution was at amino acid position 31 (n=27; 47%). Overall prevalence of baseline NS3/4A protease inhibitor resistance-associated substitutions was 12% (21/169). The most prevalent NS3 resistance-associated substitutions were at positions 55 (5/10) and 168 (3/10) in genotype 1a, position 56 in genotype 1b (3/5) and genotype 2 (3/3), and at position 168 in genotype 4 (3/3).

SVR12 was achieved in 18 of 19 (95%) subjects who had baseline nucleotide analog NS5B polymerase inhibitor resistance-associated substitutions in POLARIS-1, including 2 subjects who had virus with the S282T nucleotide analog NS5B polymerase inhibitor resistance-associated substitution in addition to NS5A resistance-associated substitutions at baseline. In POLARIS-4, a total of 14 subjects had virus with nucleotide analog NS5B polymerase inhibitor resistance-associated substitutions at baseline and all achieved SVR12.

Cross Resistance

Cross-resistance is possible between HCV NS3/4A protease inhibitors and between HCV NS5A inhibitors by class. Sofosbuvir, velpatasvir, and voxilaprevir were each active against substitutions associated with resistance to other classes of DAAs with different mechanisms of actions (e.g., voxilaprevir was fully active against virus with NS5A resistance-associated substitutions and nucleotide analog NS5B inhibitor resistance-associated substitutions).

13 NONCLINICAL TOXICOLOGY

13.1 Carcinogenesis, Mutagenesis, Impairment of Fertility

Carcinogenesis and Mutagenesis

Sofosbuvir: Sofosbuvir was not genotoxic in a battery of in vitro or in vivo assays, including bacterial mutagenicity, chromosome aberration using human peripheral blood lymphocytes, and in vivo mouse micronucleus assays.

Sofosbuvir was not carcinogenic in a 2-year mouse study (up to 200 mg/kg/day in males and 600 mg/kg/day in females) and in a 2-year rat study (up to 750 mg/kg/day), resulting in exposures of the predominant circulating metabolite GS-331007 of approximately 4 and 17 times (in male and female mice, respectively) and 9 times (in rats) the exposure in humans at the recommended human dose (RHD).

Velpatasvir: Velpatasvir was not genotoxic in a battery of in vitro or in vivo assays, including bacterial mutagenicity, chromosome aberration using human peripheral blood lymphocytes, and in vivo rat micronucleus assays.

Velpatasvir was not carcinogenic in a 6-month rasH2 transgenic mouse study (up to 1000 mg/kg/day) and a 2-year rat carcinogenicity study (up to 200 mg/kg/day). The exposure of VEL in the 2-year rat study was approximately 6 times the exposure in humans at the RHD.

Voxilaprevir: Voxilaprevir was not genotoxic in a battery of in vitro or in vivo assays, including bacterial mutagenicity, chromosome aberration using human peripheral blood lymphocytes, and in vivo rat micronucleus assays.

Carcinogenicity studies for voxilaprevir have not been conducted.

Impairment of Fertility

Sofosbuvir: Sofosbuvir had no effects on embryo-fetal viability or on fertility when evaluated in rats. At the highest dose tested, AUC exposure to the predominant circulating metabolite GS-331007 was approximately 4 times the exposure in humans at the RHD.

Velpatasvir: Velpatasvir had no effects on embryo-fetal viability or on fertility when evaluated in rats. At the highest dose tested, velpatasvir exposure was approximately 4 times the exposure in humans at the RHD.

Voxilaprevir: Voxilaprevir had no effects on embryo-fetal viability or on fertility when evaluated in rats. At the highest dose tested, voxilaprevir exposure was approximately 149 times the exposure in humans at the RHD.

14 CLINICAL STUDIES

14.1 Description of Clinical Trials

The efficacy of VOSEVI was evaluated in two Phase 3 trials in DAA-experienced subjects with genotype 1, 2, 3, 4, 5, or 6 HCV infection without cirrhosis or with compensated cirrhosis, as summarized in Table 8.

Table 8 Trials Conducted With VOSEVI in DAA-Experienced Subjects With HCV Infection
Trial | Population | Study Arms and Comparator Groups (Number of Subjects Treated)
POLARIS-1 [Double-blind, placebo-controlled.] (NCT02607735) | Genotype 1, 2, 3, 4, 5, or 6 NS5A inhibitor-experienced [In clinical trials, prior NS5A inhibitor experience included daclatasvir, elbasvir, ledipasvir, ombitasvir, or velpatasvir.] , without cirrhosis or with compensated cirrhosis | VOSEVI 12 weeks (263) Placebo 12 weeks (152)
POLARIS-4 [Open-label.] (NCT02639247) | Genotype 1, 2, 3, or 4 DAA-experienced [In clinical trials, prior treatment experience included sofosbuvir with or without any of the following: peginterferon alfa/ribavirin, ribavirin, HCV NS3/4A protease inhibitor (boceprevir, simeprevir, or telaprevir).] who have not received an NS5A inhibitor, without cirrhosis or with compensated cirrhosis | VOSEVI 12 weeks (182) SOF/VEL 12 weeks (151)
DAA: direct-acting antiviral; SOF: sofosbuvir; VEL: velpatasvir

Serum HCV RNA values were measured during the clinical trials using the COBAS AmpliPrep/COBAS Taqman HCV test (version 2.0) with a lower limit of quantification (LLOQ) of 15 IU/mL. Sustained virologic response (SVR12), defined as HCV RNA less than LLOQ at 12 weeks after the cessation of treatment, was the primary endpoint in both trials. Relapse is defined as HCV RNA greater than or equal to LLOQ after end-of-treatment response among subjects who completed treatment. On-treatment virologic failure is defined as breakthrough, rebound, or non-response.

14.2 Clinical Trials in HCV DAA-Experienced Subjects

NS5A Inhibitor-Experienced Adults Without Cirrhosis or With Compensated Cirrhosis (POLARIS-1)

POLARIS-1 was a randomized, double-blind, placebo-controlled trial that evaluated 12 weeks of treatment with VOSEVI compared with 12 weeks of placebo in DAA-experienced subjects with genotype 1, 2, 3, 4, 5, or 6 HCV infection without cirrhosis or with compensated cirrhosis who previously failed a regimen containing an NS5A inhibitor. Subjects with genotype 1 HCV infection were randomized 1:1 to each group. Subjects with genotype 2, 3, 4, 5, or 6 HCV infection were enrolled to the VOSEVI group. Randomization was stratified by the presence or absence of cirrhosis.

Demographics and baseline characteristics were generally balanced across treatment groups. Of the 415 treated subjects, the median age was 59 years (range: 27 to 84); 77% of the subjects were male; 81% were White; 14% were Black; 6% were Hispanic or Latino; 33% had a baseline body mass index at least 30 kg/m^2; the majority of subjects had genotype 1 (72%) or genotype 3 (19%) HCV infection; 82% had a non-CC IL28B genotype (CT or TT); 74% had baseline HCV RNA levels at least 800,000 IU/mL; and 41% had compensated cirrhosis. In the POLARIS-1 trial, prior DAA regimens contained the following NS5A inhibitors: ledipasvir (51%), daclatasvir (27%), ombitasvir (11%), velpatasvir (7%), and elbasvir (3%).

Table 9 presents the SVR12 by HCV genotype for the POLARIS-1 trial. No subjects in the placebo group achieved SVR12.

Table 9 POLARIS-1 Trial: Virologic Outcomes by HCV Genotype in VOSEVI-Treated Subjects Without Cirrhosis or With Compensated Cirrhosis (12 Weeks After Treatment)
 | VOSEVI 12 Weeks (N=263)
 | Total (all GTs) [One subject with undetermined genotype achieved SVR12.] (N=263) | GT-1 |  |  | GT-2 (N=5) | GT-3 (N=78) | GT-4 (N=22) | GT-5 (N=1) | GT-6 (N=6)
 | Total (all GTs) [One subject with undetermined genotype achieved SVR12.] (N=263) | GT-1a (N=101) | GT-1b (N=45) | Total [Four subjects had GT-1 subtypes other than GT-1a or GT-1b; all 4 subjects achieved SVR12.] (N=150) | GT-2 (N=5) | GT-3 (N=78) | GT-4 (N=22) | GT-5 (N=1) | GT-6 (N=6)
SVR12 | 96% (253/263) | 96% (97/101) | 100% (45/45) | 97% (146/150) | 100% (5/5) | 95% (74/78) | 91% (20/22) | 100% (1/1) | 100% (6/6)
Outcome for Subjects without SVR
On-Treatment Virologic Failure | <1% (1/263) | 1% (1/101) | 0/45 | 1% (1/150) | 0/5 | 0/78 | 0/22 | 0/1 | 0/6
Relapse [The denominator for relapse is the number of subjects with HCV RNA <LLOQ at the end-of-treatment assessment.] | 2% (6/261) | 1% (1/100) | 0/45 | 1% (1/149) | 0/5 | 5% (4/78) | 5% (1/21) | 0/1 | 0/6
Other [Other includes subjects who discontinued due to adverse event, lost to follow-up, or subject withdrawal.] | 1% (3/263) | 2% (2/101) | 0/45 | 1% (2/150) | 0/5 | 0/78 | 5% (1/22) | 0/1 | 0/6
GT: genotype

DAA-Experienced Adults Without Cirrhosis or With Compensated Cirrhosis Who Had Not Received An NS5A Inhibitor (POLARIS-4)

POLARIS-4 was a randomized, open-label trial that evaluated 12 weeks of treatment with VOSEVI and 12 weeks of treatment with SOF/VEL in subjects with genotype 1, 2, 3, or 4 HCV infection without cirrhosis or with compensated cirrhosis who had previously failed a HCV DAA-containing regimen that did not include an NS5A inhibitor. Subjects whose only DAA exposure was an NS3/4A protease inhibitor were excluded. Subjects with genotype 1, 2, or 3 HCV infection were randomized 1:1 to each group. Randomization was stratified by HCV genotype and by the presence or absence of cirrhosis. Subjects with genotype 4 HCV infection were enrolled to the VOSEVI group. No subjects with genotype 5 or 6 were enrolled.

Demographics and baseline characteristics were generally balanced across treatment groups. Of the 333 treated subjects, the median age was 58 years (range: 24 to 85); 77% of the subjects were male; 87% were White, 9% were Black; 8% were Hispanic or Latino; 35% had a baseline body mass index at least 30 kg/m^2; 81% had non-CC IL28B genotypes (CT or TT); 75% had baseline HCV RNA levels at least 800,000 IU/mL; and 46% had compensated cirrhosis. In the POLARIS-4 trial, prior DAA regimens contained sofosbuvir (85%) with the following: peginterferon alfa and ribavirin or ribavirin (69%), HCV NS3/4A protease inhibitor (boceprevir, simeprevir, or telaprevir; 15%), and investigational DAA (<1%). Of the 15% of subjects without prior sofosbuvir exposure, most received investigational HCV DAAs or approved HCV NS3/4A protease inhibitors, with or without peginterferon alfa and ribavirin.

Treatment with VOSEVI for 12 weeks resulted in numerically higher SVR12 rates than treatment with sofosbuvir/velpatasvir for 12 weeks in subjects with HCV genotype 1a and 3 infection. Comparable SVR12 rates were observed in subjects with HCV genotype 1b and 2 infection treated with VOSEVI for 12 weeks or with sofosbuvir/velpatasvir for 12 weeks. No comparison data are available for HCV genotypes 4, 5, and 6. Given these data, the additional benefit of VOSEVI has not been shown over sofosbuvir/velpatasvir for these genotypes and VOSEVI is only indicated for the treatment of HCV genotypes 1a or 3 infection in adults who previously received sofosbuvir without an NS5A inhibitor.

Table 10 presents the comparative virologic outcome data for HCV genotype 1, 2, and 3 subjects with prior exposure to a sofosbuvir-containing regimen.

Table 10 POLARIS-4 Trial: Virologic Outcomes by HCV Genotype in VOSEVI-Treated Subjects* and SOF/VEL-Treated Subjects* Without Cirrhosis or With Compensated Cirrhosis (12 Weeks After Treatment)
*Subjects with prior exposure to a SOF-containing regimen | VOSEVI 12 Weeks (N=139) | SOF/VEL 12 Weeks (N=125)
Overall (Genotypes 1, 2, and 3)
SVR12 | 97% (135/139) | 88% (110/125)
Not achieving SVR12
On-treatment virologic failure | 0% (0/139) | 1% (1/125)
Relapse [The denominator for relapse is the number of subjects with HCV RNA <LLOQ at the end-of-treatment assessment.] | 1% (1/139) | 10% (13/124)
Other [Other includes subjects who discontinued due to adverse event, lost to follow-up, or subject withdrawal.] | 2% (3/139) | 1% (1/125)
Genotype 1
SVR12 | 96% (52/54) | 85% (34/40)
Not achieving SVR12
On-treatment virologic failure | 0% (0/54) | 0% (0/40)
Relapse | 2% (1/54) | 13% (5/40)
Other | 2% (1/54) | 3% (1/40)
Genotype 1a
SVR12 | 97% (35/36) | 82% (23/28)
Not achieving SVR12
On-treatment virologic failure | 0% (0/36) | 0% (0/28)
Relapse | 3% (1/36) | 18% (5/28)
Other | 0% (0/36) | 0% (0/28)
Genotype 1b
SVR12 | 94% (17/18) | 92% (11/12)
Not achieving SVR12
On-treatment virologic failure | 0% (0/18) | 0% (0/12)
Relapse | 0% (0/18) | 0% (0/12)
Other | 6% (1/18) | 8% (1/12)
Genotype 2
SVR12 | 100% (31/31) | 97% (32/33)
Not achieving SVR12
On-treatment virologic failure | 0% (0/31) | 3% (1/33)
Relapse | 0% (0/31) | 0% (0/32)
Other | 0% (0/31) | 0% (0/33)
Genotype 3
SVR12 | 96% (52/54) | 85% (44/52)
Not achieving SVR12
On-treatment virologic failure | 0% (0/54) | 0% (0/52)
Relapse | 0% (0/54) | 15% (8/52)
Other | 4% (2/54) | 0% (0/52)

In POLARIS-4, VOSEVI was administered for 12 weeks to 18 HCV genotype 4 subjects (with or without cirrhosis) who had prior exposure to a SOF-containing regimen without an NS5A inhibitor. All subjects achieved SVR12.

16 HOW SUPPLIED/STORAGE AND HANDLING

Each VOSEVI tablet contains 400 mg of sofosbuvir, 100 mg of velpatasvir, and 100 mg of voxilaprevir. The tablets are beige, capsule-shaped, film-coated, and debossed with "GSI" on one side and "" on the other side. Each bottle contains 28 tablets (NDC 61958-2401-1), polyester coil, silica gel desiccant, and is closed with a child-resistant closure.

STORAGE AND HANDLING

Store below 30 °C (86 °F). Dispense only in original container.

17 PATIENT COUNSELING INFORMATION

Advise the patient to read the FDA-approved patient labeling (Patient Information).

Risk of Hepatitis B Virus Reactivation in Patients Coinfected with HCV and HBV

Inform patients that HBV reactivation can occur in patients coinfected with HBV during or after treatment of HCV virus infection. Advise patients to tell their healthcare provider if they have a history of hepatitis B infection [see Warnings and Precautions (5.1)].

Risk of Hepatic Decompensation/Failure in Patients with Evidence of Advanced Liver Disease

Advise patients to seek medical evaluation immediately for symptoms of worsening liver problems such as nausea, tiredness, yellowing of the skin or white part of the eyes, bleeding or bruising more easily than normal, confusion, loss of appetite, diarrhea, dark or brown urine, dark or bloody stool, swelling of the stomach area (abdomen) or pain in the upper right side of the stomach area, sleepiness, or vomiting of blood [see Warnings and Precautions (5.2)].

Serious Symptomatic Bradycardia When Coadministered with Amiodarone

Advise patients to seek medical evaluation immediately for symptoms of bradycardia such as near-fainting or fainting, dizziness or lightheadedness, malaise, weakness, excessive tiredness, shortness of breath, chest pain, confusion, or memory problems [see Warnings and Precautions (5.3), Adverse Reactions (6.2), and Drug Interactions (7.3)].

Drug Interactions

Inform patients that VOSEVI may interact with other drugs. Advise patients to report to their healthcare provider the use of any other prescription or nonprescription medication or herbal products including St. John's wort [see Warnings and Precautions (5.3, 5.4) and Drug Interactions (7)].

Administration

Advise patients to take VOSEVI once daily on a regular dosing schedule with food. Inform patients that it is important not to miss or skip doses and to take VOSEVI for the duration that is recommended by the physician.

Manufactured and distributed by:
Gilead Sciences, Inc.
Foster City, CA 94404

VOSEVI, ATRIPLA, GENVOYA, HARVONI, and ODEFSEY are trademarks of Gilead Sciences, Inc., or its related companies. All other trademarks referenced herein are the property of their respective owners.

© 2019 Gilead Sciences, Inc. All rights reserved.
209195-GS-003

Patient Information
VOSEVI® (voh-SEV-ee)
(sofosbuvir, velpatasvir, and voxilaprevir) tablets

What is the most important information I should know about VOSEVI?
VOSEVI can cause serious side effects, including,
Hepatitis B virus reactivation: Before starting treatment with VOSEVI, your healthcare provider will do blood tests to check for hepatitis B virus infection. If you have ever had hepatitis B virus infection, the hepatitis B virus could become active again during or after treatment of hepatitis C virus with VOSEVI. Hepatitis B virus becoming active again (called reactivation) may cause serious liver problems including liver failure and death. Your healthcare provider will monitor you if you are at risk for hepatitis B virus reactivation during treatment and after you stop taking VOSEVI.
For more information about side effects, see the section "What are the possible side effects of VOSEVI?"

What is VOSEVI?
VOSEVI is a prescription medicine used to treat adults with chronic (lasting a long time) hepatitis C virus (HCV) infection without cirrhosis or with compensated cirrhosis who have:

- genotype 1, 2, 3, 4, 5, or 6 infection and have previously been treated with an HCV regimen containing an NS5A inhibitor.
- genotype 1a or 3 infection and have previously been treated with an HCV regimen containing sofosbuvir without an NS5A inhibitor.

It is not known if VOSEVI is safe and effective in children.

Do not take VOSEVI: if you also take any medicines that contain rifampin (Rifater®, Rifamate®, Rimactane®, Rifadin®)

Before taking VOSEVI, tell your healthcare provider about all your medical conditions, including if you:

- have ever had hepatitis B infection
- have liver problems other than hepatitis C infection
- are pregnant or plan to become pregnant. It is not known if VOSEVI will harm your unborn baby.
- are breastfeeding or plan to breastfeed. It is not known if VOSEVI passes into your breast milk. Talk to your healthcare provider about the best way to feed your baby if you take VOSEVI.

Tell your healthcare provider about all of the medicines you take, including prescription and over-the-counter medicines, vitamins, and herbal supplements. VOSEVI and other medicines may affect each other. This can cause you to have too much or not enough VOSEVI or other medicines in your body. This may affect the way VOSEVI or your other medicines work or may cause side effects.
Keep a list of your medicines to show your healthcare provider and pharmacist.

- You can ask your healthcare provider or pharmacist for a list of medicines that interact with VOSEVI.
- Do not start taking a new medicine without telling your healthcare provider. Your healthcare provider can tell you if it is safe to take VOSEVI with other medicines.

How should I take VOSEVI?

- Take VOSEVI exactly as your healthcare provider tells you. Do not change your dose unless your healthcare provider tells you to.
- Do not stop taking VOSEVI without first talking with your healthcare provider.
- Take 1 VOSEVI tablet by mouth each day on a regular schedule.
- Take VOSEVI with food.
- If you need to take an antacid medicine that contains aluminum or magnesium, take it either 4 hours before or 4 hours after you take your dose of VOSEVI.
- It is important that you do not miss or skip doses of VOSEVI during treatment.
- If you take too much VOSEVI, call your healthcare provider or go to the nearest hospital emergency room right away.

What are the possible side effects of VOSEVI?
VOSEVI may cause serious side effects, including:

- Hepatitis B virus (HBV) reactivation. See "What is the most important information I should know about VOSEVI?"
- In people who had or have advanced liver problems before starting treatment with VOSEVI: rare risk of worsening liver problems, liver failure and death. Your healthcare provider will check you for signs and symptoms of worsening liver problems during treatment with VOSEVI. Tell your healthcare provider right away if you have any of the following signs and symptoms:

- nausea
- tiredness
- yellowing of your skin or white part of your eyes
- bleeding or bruising more easily than normal
- confusion
- dark, black, or bloody stool
- loss of appetite

- diarrhea
- dark or brown (tea-colored) urine
- swelling of your stomach area (abdomen) or pain on the upper right side of your stomach area
- sleepiness
- vomiting of blood
- lightheadedness

- Slow heart rate (bradycardia). VOSEVI treatment may result in slowing of the heart rate along with other symptoms when taken with amiodarone (Cordarone®, Nexterone®, Pacerone®), a medicine used to treat certain heart problems. In some cases, bradycardia has led to death or the need for a heart pacemaker when amiodarone is taken with medicines similar to VOSEVI that contain sofosbuvir. Get medical help right away if you take amiodarone with VOSEVI and get any of the following symptoms:

- fainting or near-fainting
- dizziness or lightheadedness
- not feeling well
- weakness
- extreme tiredness

- shortness of breath
- chest pains
- confusion
- memory problems

- The most common side effects of VOSEVI include headache, tiredness, diarrhea, and nausea.

These are not all the possible side effects of VOSEVI.
Call your doctor for medical advice about side effects. You may report side effects to FDA at 1-800-FDA-1088.

How should I store VOSEVI?

- Store VOSEVI below 86 °F (30 °C).
- Keep VOSEVI in its original container.

Keep VOSEVI and all medicines out of the reach of children.

General information about the safe and effective use of VOSEVI
Medicines are sometimes prescribed for purposes other than those listed in a Patient Information leaflet. Do not use VOSEVI for a condition for which it was not prescribed. Do not give VOSEVI to other people, even if they have the same symptoms that you have. It may harm them.
You can ask your pharmacist or healthcare provider for information about VOSEVI that is written for health professionals.

What are the ingredients in VOSEVI?
Active ingredients: sofosbuvir, velpatasvir, and voxilaprevir
Inactive ingredients: colloidal silicon dioxide, copovidone, croscarmellose sodium, lactose monohydrate, magnesium stearate, and microcrystalline cellulose.
The tablet film-coat contains: ferrosoferric oxide, iron oxide red, iron oxide yellow, polyethylene glycol, polyvinyl alcohol, talc, and titanium dioxide.
Manufactured and distributed by:
Gilead Sciences, Inc., Foster City, CA 94404
For more information, call 1-800-445-3235 or go to www.VOSEVI.com.
VOSEVI is a trademark of Gilead Sciences, Inc., or its related companies. All other trademarks referenced herein are the property of their respective owners.
©2019 Gilead Sciences, Inc. All rights reserved.
209195-GS-003

This Patient Information has been approved by the U.S. Food and Drug Administration.

Revised: 11/2019

PRINCIPAL DISPLAY PANEL - 28 Tablet Bottle Label

NDC 61958-2401-1
28 tablets

Vosevi™
(sofosbuvir, velpatasvir,
and voxilaprevir) tablets
400 mg / 100 mg / 100 mg

Take 1 tablet once daily

Note to pharmacist:
Do not cover ALERT box with pharmacy label.

ALERT: Find out about medicines that
should NOT be taken with Vosevi